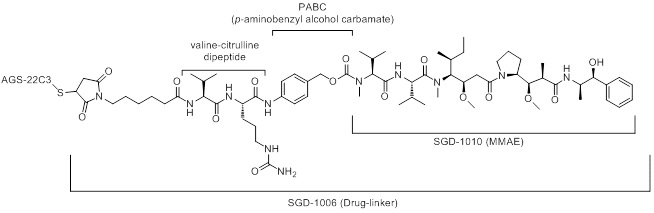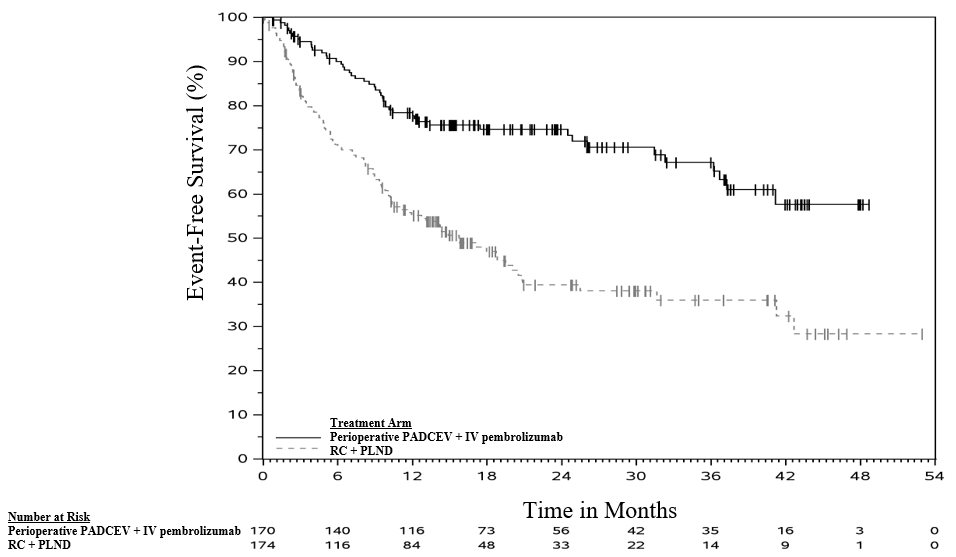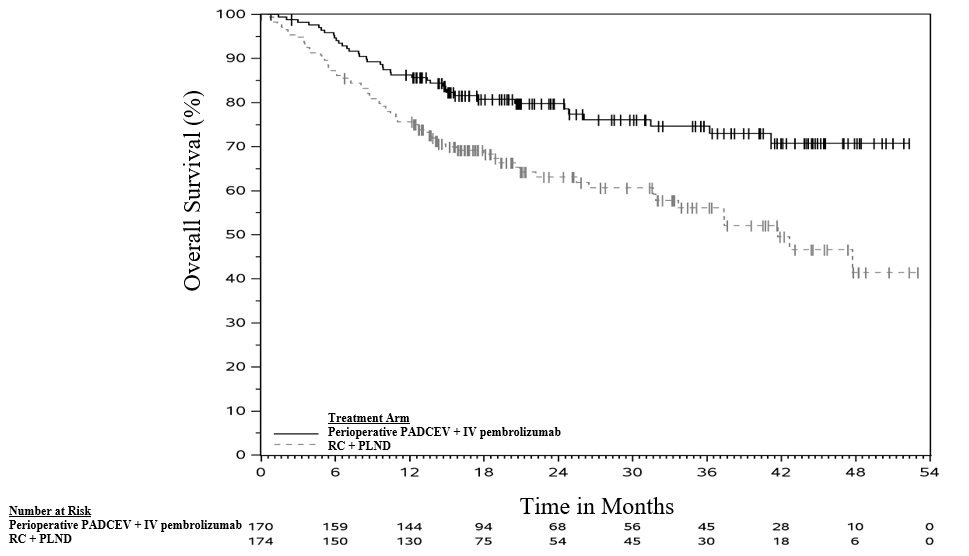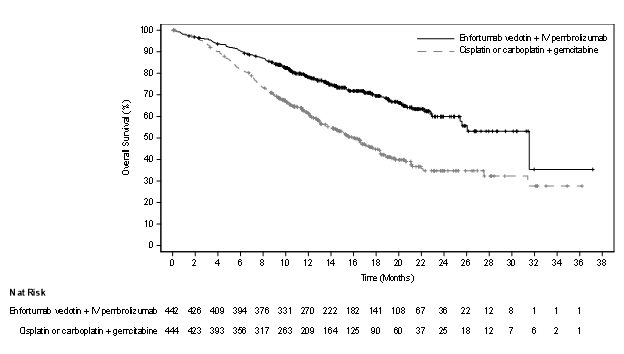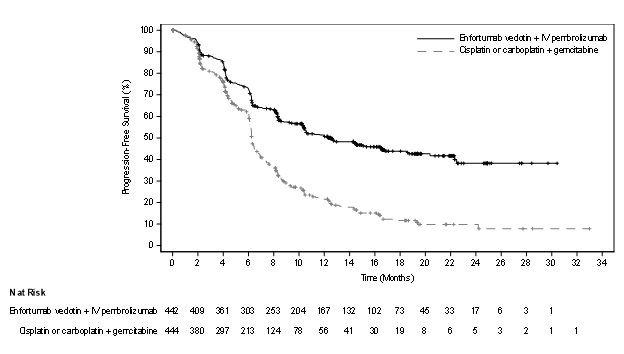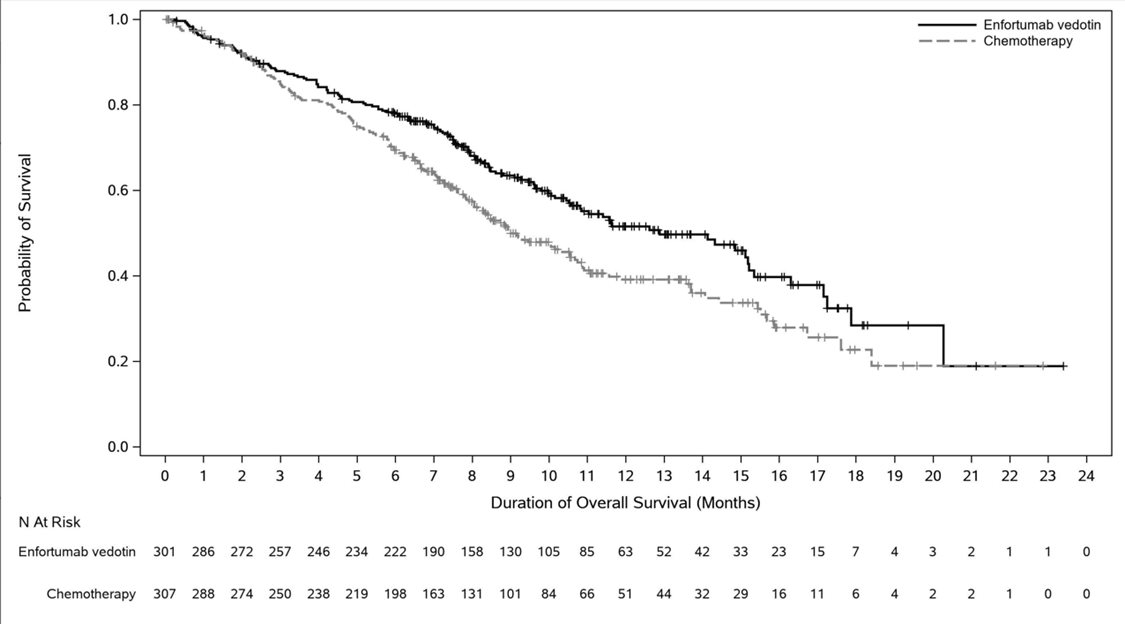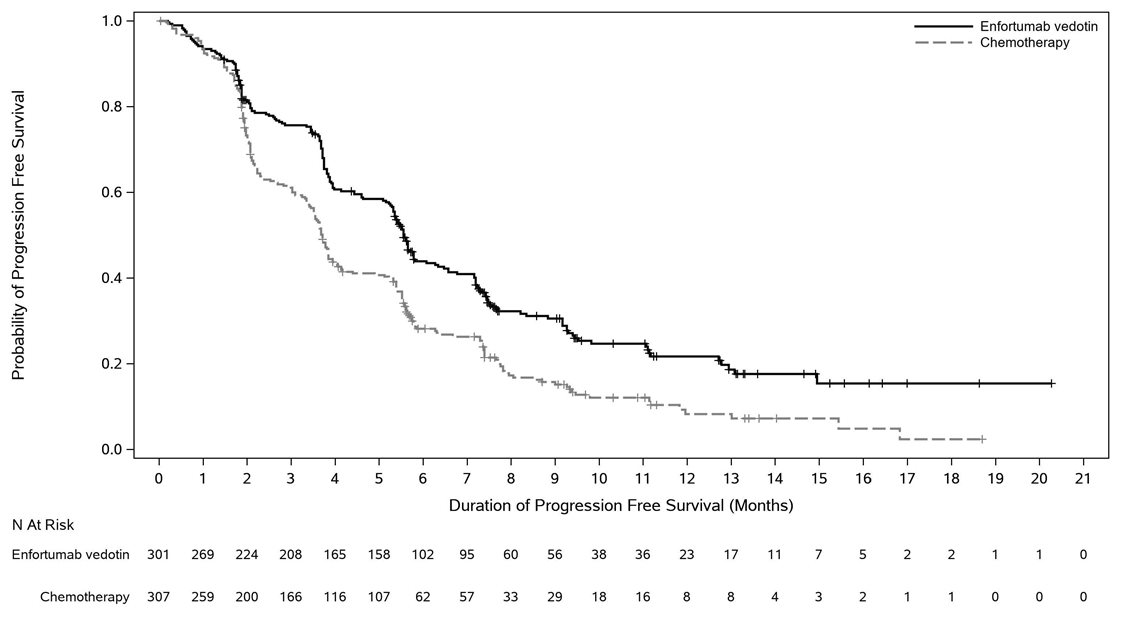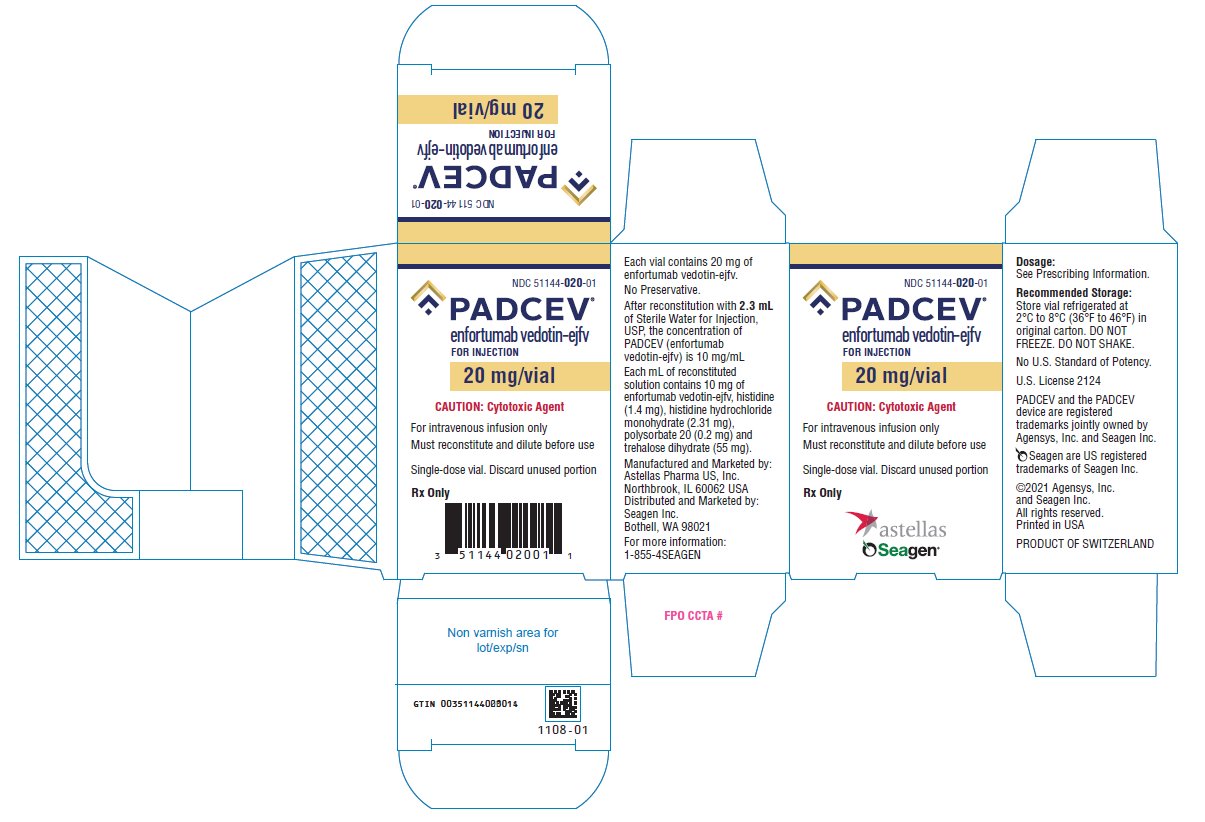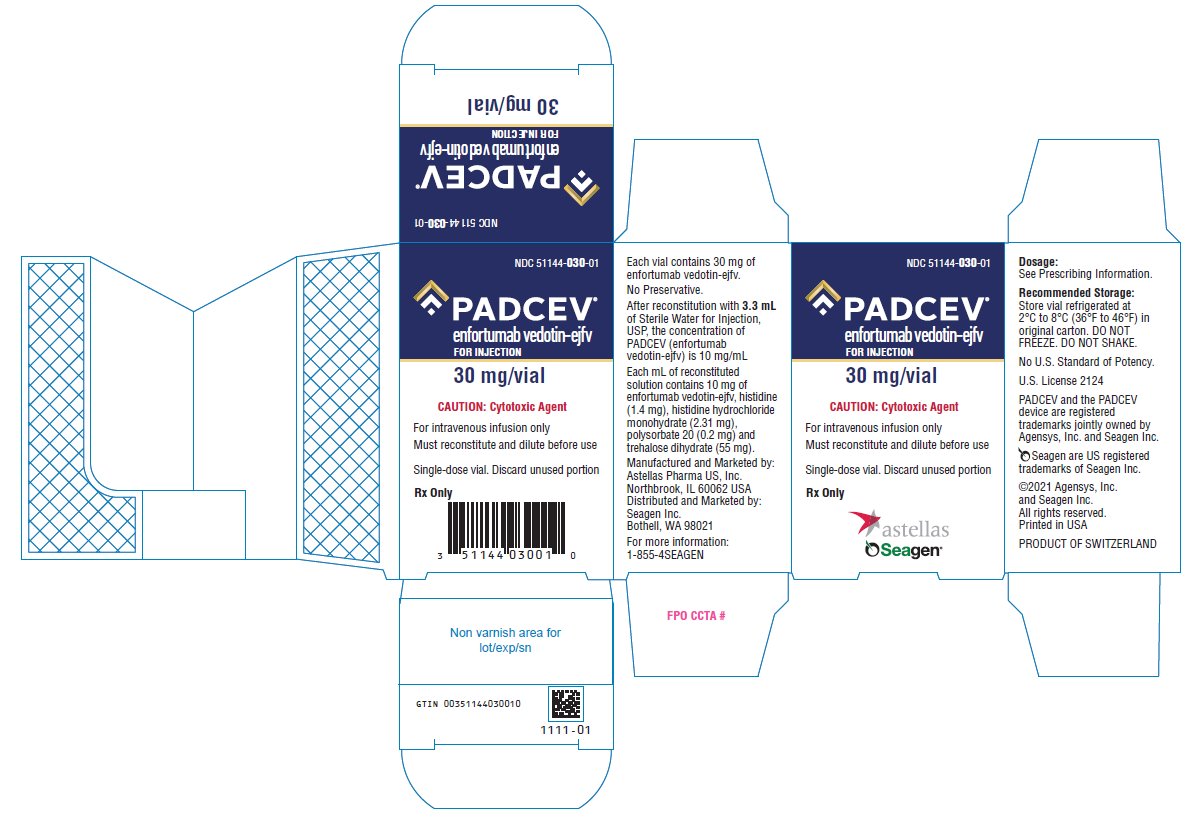 DRUG LABEL: PADCEV
NDC: 51144-020 | Form: INJECTION, POWDER, LYOPHILIZED, FOR SOLUTION
Manufacturer: SEAGEN INC.
Category: prescription | Type: HUMAN PRESCRIPTION DRUG LABEL
Date: 20251121

ACTIVE INGREDIENTS: ENFORTUMAB VEDOTIN 20 mg/2 mL
INACTIVE INGREDIENTS: HISTIDINE 2.8 mg/2 mL; HISTIDINE HYDROCHLORIDE MONOHYDRATE 4.62 mg/2 mL; TREHALOSE DIHYDRATE 110 mg/2 mL; POLYSORBATE 20 0.4 mg/2 mL

HIGHLIGHTS OF PRESCRIBING INFORMATION

These highlights do not include all the information needed to use PADCEV safely and effectively. See full prescribing information for PADCEV.
PADCEV® (enfortumab vedotin-ejfv) for injection, for intravenous use
Initial U.S. Approval: 2019

RECENT MAJOR CHANGES

Indications and Usage (1) 11/2025

Dosage and Administration (2.1) 11/2025

Warnings and Precautions (5.1), (5.3), (5.4) 11/2025

WARNING: SERIOUS SKIN REACTIONS

See full prescribing information for complete boxed warning.

- PADCEV can cause severe and fatal cutaneous adverse reactions, including Stevens-Johnson syndrome (SJS) and Toxic Epidermal Necrolysis (TEN).
- Immediately withhold PADCEV and consider referral for specialized care for suspected SJS or TEN or severe skin reactions.
- Permanently discontinue PADCEV in patients with confirmed SJS or TEN; or Grade 4 or recurrent Grade 3 skin reactions. (2.2), (5.1), (6.1)

1 INDICATIONS AND USAGE

PADCEV is a Nectin-4-directed antibody and microtubule inhibitor conjugate indicated:

- in combination with pembrolizumab or pembrolizumab and berahyaluronidase alfa-pmph, as neoadjuvant treatment and then continued after cystectomy as adjuvant treatment, for the treatment of adult patients with muscle invasive bladder cancer (MIBC) who are ineligible for cisplatin-containing chemotherapy. (1)
- in combination with pembrolizumab or pembrolizumab and berahyaluronidase alfa-pmph, for the treatment of adult patients with locally advanced or metastatic urothelial cancer (mUC). (1)
- as a single agent for the treatment of adult patients with locally advanced or mUC who:
  - have previously received a programmed death receptor-1 (PD-1) or programmed death-ligand 1 (PD-L1) inhibitor and platinum-containing chemotherapy, or
  - are ineligible for cisplatin-containing chemotherapy and have previously received one or more prior lines of therapy. (1)

2 DOSAGE AND ADMINISTRATION

- For intravenous infusion only. Do not administer PADCEV as an intravenous push or bolus. Do not mix with, or administer as an infusion with, other medicinal products. (2.3)
- MIBC: The recommended dose of PADCEV in combination with pembrolizumab or pembrolizumab and berahyaluronidase alfa-pmph is 1.25 mg/kg (up to a maximum dose of 125 mg) given as an intravenous infusion over 30 minutes. PADCEV is administered as neoadjuvant treatment on Days 1 and 8 of each 21-day cycle for 3 cycles or until disease progression that precludes curative intent cystectomy or unacceptable toxicity, followed by adjuvant treatment on Days 1 and 8 of each 21-day cycle for 6 cycles or until disease recurrence or unacceptable toxicity. (2.1)
- Locally Advanced or mUC: The recommended dose of PADCEV in combination with pembrolizumab or pembrolizumab and berahyaluronidase alfa-pmph is 1.25 mg/kg (up to a maximum dose of 125 mg) given as an intravenous infusion over 30 minutes on Days 1 and 8 of a 21-day cycle until disease progression or unacceptable toxicity. (2.1)
- The recommended dose of PADCEV as a single agent is 1.25 mg/kg (up to a maximum dose of 125 mg) given as an intravenous infusion over 30 minutes on Days 1, 8, and 15 of a 28-day cycle until disease progression or unacceptable toxicity. (2.1)
- Avoid use in patients with moderate or severe hepatic impairment. (8.6)

3 DOSAGE FORMS AND STRENGTHS

For Injection: 20 mg and 30 mg of enfortumab vedotin-ejfv as a lyophilized powder in a single-dose vial for reconstitution. (3)

4 CONTRAINDICATIONS

None. (4)

5 WARNINGS AND PRECAUTIONS

- Hyperglycemia: Diabetic ketoacidosis may occur in patients with and without preexisting diabetes mellitus, which may be fatal. Closely monitor blood glucose levels in patients with, or at risk for, diabetes mellitus or hyperglycemia. Withhold PADCEV if blood glucose is >250 mg/dL. (2.2, 5.2)
- Pneumonitis/Interstitial Lung Disease (ILD): Severe, life-threatening or fatal pneumonitis/ILD may occur. Withhold PADCEV for Grade 2 pneumonitis/ILD and consider dose reduction. Permanently discontinue PADCEV for Grade 3 or 4 pneumonitis/ILD. (2.2, 5.3)
- Peripheral Neuropathy: Monitor patients for new or worsening peripheral neuropathy and consider dose interruption, dose reduction, or discontinuation of PADCEV. (2.2, 5.4)
- Ocular Disorders: Ocular disorders, including vision changes, may occur. Monitor patients for signs or symptoms of ocular disorders. Consider prophylactic artificial tears for dry eyes and treatment with ophthalmic topical steroids after an ophthalmic exam. Consider dose interruption or dose reduction of PADCEV when symptomatic ocular disorders occur. (5.5)
- Infusion Site Extravasation: Ensure adequate venous access prior to administration. Monitor the infusion site during PADCEV administration and stop the infusion immediately for suspected extravasation. (5.6)
- Embryo-Fetal Toxicity: PADCEV can cause fetal harm. Advise of the potential risk to a fetus and to use effective contraception. (5.7, 8.1, 8.3)

6 ADVERSE REACTIONS

The most common adverse reactions, including laboratory abnormalities, (≥20%) were:

- PADCEV in combination with intravenous pembrolizumab for the treatment of MIBC: increased glucose, decreased hemoglobin, increased aspartate aminotransferase, rash, increased alanine aminotransferase, fatigue, pruritus, increased creatinine, decreased sodium, decreased lymphocytes, peripheral neuropathy, increased potassium, alopecia, dysgeusia, diarrhea, decreased appetite, constipation, nausea, decreased phosphate, urinary tract infection, dry eye, and decreased weight. (6.1)
- PADCEV in combination with intravenous pembrolizumab for the treatment of locally advanced or mUC: increased aspartate aminotransferase, increased creatinine, rash, increased glucose, peripheral neuropathy, increased lipase, decreased lymphocytes, increased alanine aminotransferase, decreased hemoglobin, fatigue, decreased sodium, decreased phosphate, decreased albumin, pruritus, diarrhea, alopecia, decreased weight, decreased appetite, increased urate, decreased neutrophils, decreased potassium, dry eye, nausea, constipation, increased potassium, dysgeusia, urinary tract infection, and decreased platelets. (6.1)
- PADCEV as a single agent: increased glucose, increased aspartate aminotransferase, decreased lymphocytes, increased creatinine, rash, fatigue, peripheral neuropathy, decreased albumin, decreased hemoglobin, alopecia, decreased appetite, decreased neutrophils, decreased sodium, increased alanine aminotransferase, decreased phosphate, diarrhea, nausea, pruritus, increased urate, dry eye, dysgeusia, constipation, increased lipase, decreased weight, decreased platelets, abdominal pain, and dry skin. (6.1)

To report SUSPECTED ADVERSE REACTIONS, contact Astellas Pharma US, Inc. at 1-800-727-7003 or FDA at 1-800-FDA-1088 or www.fda.gov/medwatch.

7 DRUG INTERACTIONS

Concomitant use of dual P-gp and strong CYP3A4 inhibitors with PADCEV may increase the exposure to monomethyl auristatin E (MMAE). (7.1)

8 USE IN SPECIFIC POPULATIONS

- Lactation: Advise women not to breastfeed. (8.2)

FULL PRESCRIBING INFORMATION

WARNING: SERIOUS SKIN REACTIONS

- PADCEV can cause severe and fatal cutaneous adverse reactions including Stevens-Johnson syndrome (SJS) and Toxic Epidermal Necrolysis (TEN), which occurred predominantly during the first cycle of treatment, but may occur later.
- Closely monitor patients for skin reactions.
- Immediately withhold PADCEV and consider referral for specialized care for suspected SJS or TEN or severe skin reactions.
- Permanently discontinue PADCEV in patients with confirmed SJS or TEN; or Grade 4 or recurrent Grade 3 skin reactions [see Dosage and Administration (2.2), Warnings and Precautions (5.1), and Adverse Reactions (6.1)].

1 INDICATIONS AND USAGE

PADCEV®, in combination with pembrolizumab or pembrolizumab and berahyaluronidase alfa-pmph, as neoadjuvant treatment and then continued after cystectomy as adjuvant treatment, is indicated for the treatment of adult patients with muscle invasive bladder cancer (MIBC) who are ineligible for cisplatin-containing chemotherapy.

PADCEV®, in combination with pembrolizumab or pembrolizumab and berahyaluronidase alfa-pmph, is indicated for the treatment of adult patients with locally advanced or metastatic urothelial cancer (mUC).

PADCEV, as a single agent, is indicated for the treatment of adult patients with locally advanced or mUC who:

- have previously received a programmed death receptor-1 (PD-1) or programmed death-ligand 1 (PD-L1) inhibitor and platinum-containing chemotherapy, or
- are ineligible for cisplatin-containing chemotherapy and have previously received one or more prior lines of therapy.

2 DOSAGE AND ADMINISTRATION

2.1 Recommended Dosage

The recommended dosages for PADCEV in combination with pembrolizumab or pembrolizumab and berahyaluronidase alfa-pmph, and PADCEV as a single agent are presented in Table 1 and Table 2.

Administer PADCEV as an intravenous infusion over 30 minutes as recommended [see Instructions for Preparation and Administration (2.3)]. Administer PADCEV prior to pembrolizumab or pembrolizumab and berahyaluronidase alfa-pmph if administering on the same day.

Table 1. Recommended Dosages for PADCEV in combination with pembrolizumab or pembrolizumab and berahyaluronidase alfa-pmph [Administer PADCEV prior to pembrolizumab or pembrolizumab and berahyaluronidase alfa-pmph if administering on the same day. For the recommended dosage of pembrolizumab or pembrolizumab and berahyaluronidase alfa-pmph, refer to the respective Prescribing Information.]
Indication | Recommended PADCEV Dosage | Duration of Therapy
Neoadjuvant and Adjuvant Muscle Invasive Bladder Cancer (MIBC) | PADCEV 1.25 mg/kg (up to a maximum of 125 mg for patients ≥100 kg) on Days 1 and 8 of a 21-day cycle. | Neoadjuvant: 3 cycles or until disease progression that precludes curative intent cystectomy or unacceptable toxicity.; Adjuvant: 6 cycles or until disease recurrence or unacceptable toxicity.
Locally advanced or metastatic Urothelial Cancer (mUC) | PADCEV 1.25 mg/kg (up to a maximum of 125 mg for patients ≥100 kg) on Days 1 and 8 of a 21-day cycle. | Until disease progression or unacceptable toxicity.

Table 2. Recommended Dosages for PADCEV as a single agent
Indication | Recommended PADCEV Dosage | Duration of Therapy
Locally advanced or metastatic Urothelial Cancer (mUC) | PADCEV 1.25 mg/kg (up to a maximum of 125 mg for patients ≥100 kg) on Days 1, 8, and 15 of a 28-day cycle. | Until disease progression or unacceptable toxicity.

2.2 Dose Modifications

Table 3. Dose Modifications
Adverse Reaction | Severity [Grade 1 is mild, Grade 2 is moderate, Grade 3 is severe, Grade 4 is life-threatening.] | Dose Modification
Skin Reactions; [see Boxed Warning, Warnings and Precautions (5.1)] | For persistent or recurrent Grade 2 skin reactions | Consider withholding until Grade ≤1, then resume treatment at the same dose level or dose reduce by one dose level.
Skin Reactions; [see Boxed Warning, Warnings and Precautions (5.1)] | Grade 3 skin reactions | Withhold until Grade ≤1, then resume treatment at the same dose level or dose reduce by one dose level.
Skin Reactions; [see Boxed Warning, Warnings and Precautions (5.1)] | Suspected SJS or TEN | Immediately withhold, consult a specialist to confirm the diagnosis. If not SJS/TEN, see Grade 2-4 skin reactions.
Skin Reactions; [see Boxed Warning, Warnings and Precautions (5.1)] | Confirmed SJS or TEN; Grade 4 or recurrent Grade 3 skin reactions | Permanently discontinue.
Hyperglycemia; [see Warnings and Precautions (5.2)] | Blood glucose >250 mg/dL | Withhold until elevated blood glucose has improved to ≤250 mg/dL, then resume treatment at the same dose level.
Pneumonitis/Interstitial Lung Disease (ILD); [see Warnings and Precautions (5.3)] | Grade 2 | Withhold until Grade ≤1, then resume treatment at the same dose level or consider dose reduction by one dose level.
Pneumonitis/Interstitial Lung Disease (ILD); [see Warnings and Precautions (5.3)] | Grade ≥3 | Permanently discontinue.
Peripheral Neuropathy; [see Warnings and Precautions (5.4)] | Grade 2 | Withhold until Grade ≤1, then resume treatment at the same dose level (if first occurrence). For a recurrence, withhold until Grade ≤1, then resume treatment reduced by one dose level.
Peripheral Neuropathy; [see Warnings and Precautions (5.4)] | Grade ≥3 | Permanently discontinue.
Other Nonhematologic Toxicity; [see Adverse Reactions (6)] | Grade 3 | Withhold until Grade ≤1, then resume treatment at the same dose level or consider dose reduction by one dose level.
Other Nonhematologic Toxicity; [see Adverse Reactions (6)] | Grade 4 | Permanently discontinue.
Hematologic Toxicity; [see Adverse Reactions (6)] | Grade 3, or Grade 2 thrombocytopenia | Withhold until Grade ≤1, then resume treatment at the same dose level or consider dose reduction by one dose level.
Hematologic Toxicity; [see Adverse Reactions (6)] | Grade 4 | Withhold until Grade ≤1, then reduce dose by one dose level or discontinue treatment.

Table 4. Recommended Dose Reduction Schedule
Dose Reduction Schedule | Dose Level
Starting dose | 1.25 mg/kg up to 125 mg
First dose reduction | 1 mg/kg up to 100 mg
Second dose reduction | 0.75 mg/kg up to 75 mg
Third dose reduction | 0.5 mg/kg up to 50 mg

2.3 Instructions for Preparation and Administration

- Administer PADCEV as an intravenous infusion only.
- PADCEV is a hazardous drug. Follow applicable special handling and disposal procedures.^1

Prior to administration, the PADCEV vial is reconstituted with Sterile Water for Injection (SWFI). The reconstituted solution is subsequently diluted in an intravenous infusion bag containing either 5% Dextrose Injection, USP, 0.9% Sodium Chloride Injection, USP, or Lactated Ringer’s Injection, USP.

Reconstitution in Single-Dose Vial

1. Follow procedures for proper handling and disposal of anticancer drugs.
2. Use appropriate aseptic technique for reconstitution and preparation of dosing solutions.
3. Calculate the recommended dose based on the patient’s weight to determine the number and strength (20 mg or 30 mg) of vials needed.
4. Reconstitute each vial as follows and, if possible, direct the stream of SWFI along the walls of the vial and not directly onto the lyophilized powder:
  a. 20 mg vial: Add 2.3 mL of SWFI, resulting in 10 mg/mL PADCEV.
  b. 30 mg vial: Add 3.3 mL of SWFI, resulting in 10 mg/mL PADCEV.
5. Slowly swirl each vial until the contents are completely dissolved. Allow the reconstituted vial(s) to settle for at least 1 minute until the bubbles are gone. DO NOT SHAKE THE VIAL. Do not expose to direct sunlight.
6. Parenteral drug products should be inspected visually for particulate matter and discoloration prior to administration, whenever solution and container permit. The reconstituted solution should be clear to slightly opalescent, colorless to light yellow, and free of visible particles. Discard any vial with visible particles or discoloration.
7. Based upon the calculated dose amount, the reconstituted solution from the vial(s) should be added to the infusion bag immediately. This product does not contain a preservative. If not used immediately, reconstituted vials may be stored for up to 24 hours in refrigeration at 2°C to 8°C (36°F to 46°F). DO NOT FREEZE. Discard unused vials with reconstituted solution beyond the recommended storage time.

Dilution in Infusion Bag

1. Withdraw the calculated dose amount of reconstituted solution from the vial(s) and transfer into an infusion bag.
2. Dilute PADCEV with either 5% Dextrose Injection, 0.9% Sodium Chloride Injection, or Lactated Ringer's Injection. The infusion bag size should allow enough diluent to achieve a final concentration of 0.3 mg/mL to 4 mg/mL PADCEV.
3. Mix diluted solution by gentle inversion. DO NOT SHAKE THE BAG. Do not expose to direct sunlight.
4. Visually inspect the infusion bag for any particulate matter or discoloration prior to use. The reconstituted solution should be clear to slightly opalescent, colorless to light yellow, and free of visible particles. DO NOT USE the infusion bag if particulate matter or discoloration is observed.
5. Discard any unused portion left in the single-dose vials.

Administration

1. Immediately administer the infusion over 30 minutes through an intravenous line.
2. If the infusion is not administered immediately, the prepared infusion bag should not be stored longer than 8 hours at 2°C to 8°C (36°F to 46°F). DO NOT FREEZE.

DO NOT administer PADCEV as an intravenous push or bolus.

DO NOT mix PADCEV with, or administer as an infusion with, other medicinal products.

3 DOSAGE FORMS AND STRENGTHS

For Injection: 20 mg and 30 mg of enfortumab vedotin-ejfv as a white to off-white lyophilized powder in a single-dose vial for reconstitution.

4 CONTRAINDICATIONS

None.

5 WARNINGS AND PRECAUTIONS

5.1 Skin Reactions

Severe cutaneous adverse reactions, including fatal cases of SJS or TEN occurred in patients treated with PADCEV. SJS and TEN occurred predominantly during the first cycle of treatment but may occur later.

Skin reactions occurred in 61% (all grades) of the 167 patients treated with PADCEV in combination with intravenous pembrolizumab for the treatment of MIBC in clinical trials. The majority of the skin reactions that occurred with combination therapy included rash and maculo-papular rash. Grade 3-4 skin reactions occurred in 10% of patients (Grade 3: 9%, Grade 4: 1.2%), including rash, maculo-papular rash, toxic skin eruption, dermatitis exfoliative generalized, erythema, exfoliative rash, skin toxicity, toxic epidermal necrolysis, and toxic erythema of chemotherapy. A fatal reaction of toxic epidermal necrolysis occurred in one patient (0.6%). The median time to onset of severe skin reactions was 0.6 months (range: 0.2 to 8.8 months). Skin reactions led to discontinuation of PADCEV in 10% of patients [see Adverse Reactions (6.1)]. Of the patients who experienced a skin reaction and had data regarding resolution (n=102), 83% had complete resolution and 17% had residual skin reactions at their last evaluation. Of the patients with residual skin reactions at last evaluation, 29% (5/17) had Grade ≥2 skin reactions.

Skin reactions occurred in 70% (all grades) of the 564 patients treated with PADCEV in combination with intravenous pembrolizumab for the treatment of locally advanced or mUC in clinical trials. When PADCEV was given in combination with intravenous pembrolizumab, the incidence of skin reactions, including severe events, occurred at a higher rate compared to PADCEV as a single agent. The majority of the skin reactions that occurred with combination therapy included maculo-papular rash, macular rash, and papular rash. Grade 3-4 skin reactions occurred in 17% of patients (Grade 3: 16%, Grade 4: 1%), including maculo-papular rash, bullous dermatitis, dermatitis, exfoliative dermatitis, pemphigoid, rash, erythematous rash, macular rash, and papular rash. A fatal reaction of bullous dermatitis occurred in one patient (0.2%). The median time to onset of severe skin reactions was 1.7 months (range: 0.1 to 17.2 months). Skin reactions led to discontinuation of PADCEV in 6% of patients [see Adverse Reactions (6.1)]. Of the patients who experienced a skin reaction and had data regarding resolution (n=391), 59% had complete resolution and 41% had residual skin reactions at their last evaluation. Of the patients with residual skin reactions at last evaluation, 27% (43/159) had Grade ≥2 skin reactions.

Skin reactions occurred in 58% (all grades) of the 720 patients treated with PADCEV as a single agent in clinical trials. Twenty-three percent (23%) of patients had maculo-papular rash and 34% had pruritus. Grade 3-4 skin reactions occurred in 14% of patients, including maculo-papular rash, erythematous rash, rash or drug eruption, symmetrical drug-related intertriginous and flexural exanthema (SDRIFE), bullous dermatitis, exfoliative dermatitis, and palmar-plantar erythrodysesthesia. The median time to onset of severe skin reactions was 0.6 months (range: 0.1 to 8 months). Among patients experiencing a skin reaction leading to dose interruption who then restarted PADCEV (n=75), 24% of patients restarting at the same dose and 24% of patients restarting at a reduced dose experienced recurrent severe skin reactions. Skin reactions led to discontinuation of PADCEV in 3.1% of patients [see Adverse Reactions (6.1)]. Of the patients who experienced a skin reaction and had data regarding resolution (n=328), 58% had complete resolution and 42% had residual skin reactions at their last evaluation. Of the patients with residual skin reactions at last evaluation, 39% (53/137) had Grade ≥2 skin reactions.

Monitor patients closely throughout treatment for skin reactions. Consider topical corticosteroids and antihistamines, as clinically indicated.

For persistent or recurrent Grade 2 skin reactions, consider withholding PADCEV until Grade ≤1. Withhold PADCEV and refer for specialized care for suspected SJS, TEN or for Grade 3 skin reactions.

Permanently discontinue PADCEV in patients with confirmed SJS or TEN; or Grade 4 or recurrent Grade 3 skin reactions [see Dosage and Administration (2.2)].

5.2 Hyperglycemia

Hyperglycemia and diabetic ketoacidosis (DKA), including fatal events, occurred in patients with and without pre‑existing diabetes mellitus, treated with PADCEV.

Patients with baseline hemoglobin A1C ≥8% were excluded from clinical trials.

In clinical trials of PADCEV as a single agent, 17% of the 720 patients treated with PADCEV developed hyperglycemia of any grade; 7% of patients developed Grade 3-4 hyperglycemia (Grade 3: 6.5%, Grade 4: 0.6%). Fatal events of hyperglycemia and diabetic ketoacidosis occurred in one patient each (0.1%). The incidence of Grade 3-4 hyperglycemia increased consistently in patients with higher body mass index and in patients with higher baseline A1C. The median time to onset of hyperglycemia was 0.5 months (range: 0 to 20 months). Hyperglycemia led to discontinuation of PADCEV in 0.7% of patients [see Adverse Reactions (6.1)]. Five percent (5%) of patients required initiation of insulin therapy for treatment of hyperglycemia. Of the patients who initiated insulin therapy for treatment of hyperglycemia, 66% (23/35) discontinued insulin by the time of last evaluation.

Closely monitor blood glucose levels in patients with, or at risk for, diabetes mellitus or hyperglycemia.

If blood glucose is elevated (>250 mg/dL), withhold PADCEV [see Dosage and Administration (2.2)].

5.3 Pneumonitis/Interstitial Lung Disease (ILD)

Severe, life-threatening or fatal pneumonitis/ILD occurred in patients treated with PADCEV.

When PADCEV was given in combination with intravenous pembrolizumab for the treatment of MIBC, 4.2% of the 167 patients treated with combination therapy had pneumonitis/ILD of any grade. All events were Grade 1-2. The median time to onset of any grade pneumonitis/ILD was 2.5 months (range: 1.9 to 9.7 months).

When PADCEV was given in combination with intravenous pembrolizumab for the treatment of locally advanced or mUC, 10% of the 564 patients treated with combination therapy had pneumonitis/ILD of any grade and 4% had Grade 3-4. A fatal event of pneumonitis/ILD occurred in two patients (0.4%). The incidence of pneumonitis/ILD, including severe events, occurred at a higher rate when PADCEV was given in combination with intravenous pembrolizumab compared to PADCEV as a single agent. The median time to onset of any grade pneumonitis/ILD was 4 months (range: 0.3 to 26 months).

In clinical trials of PADCEV as a single agent, 3% of the 720 patients treated with PADCEV had pneumonitis/ILD of any grade and 0.8% had Grade 3-4. The median time to onset of any grade pneumonitis/ILD was 2.9 months (range: 0.6 to 6 months).

Monitor patients for signs and symptoms indicative of pneumonitis/ILD such as hypoxia, cough, dyspnea or interstitial infiltrates on radiologic exams. Evaluate and exclude infectious, neoplastic and other causes for such signs and symptoms through appropriate investigations.

Withhold PADCEV for patients who develop Grade 2 pneumonitis/ILD and consider dose reduction. Permanently discontinue PADCEV in all patients with Grade 3 or 4 pneumonitis/ILD [see Dosage and Administration (2.2)].

5.4 Peripheral Neuropathy

When PADCEV was given in combination with intravenous pembrolizumab for the treatment of MIBC, 39% of the 167 patients treated with combination therapy had peripheral neuropathy of any grade, 12% had Grade 2 neuropathy, and 3% had Grade 3 neuropathy. The median time to onset of Grade ≥2 peripheral neuropathy was 4.7 months (range: 0.2 to 11 months) [see Adverse Reactions (6.1)]. Of the patients who experienced neuropathy and had data regarding resolution (n=65), 32% had complete resolution, and 68% of patients had residual neuropathy at last evaluation. Of the patients with residual neuropathy at last evaluation, 27% (12/44) had Grade ≥2 neuropathy.

When PADCEV was given in combination with intravenous pembrolizumab for the treatment of locally advanced or mUC, 67% of the 564 patients treated with combination therapy had peripheral neuropathy of any grade, 36% had Grade 2 neuropathy, and 7% had Grade 3 neuropathy. The incidence of peripheral neuropathy occurred at a higher rate when PADCEV was given in combination with intravenous pembrolizumab compared to PADCEV as a single agent. The median time to onset of Grade ≥2 peripheral neuropathy was 6 months (range: 0.3 to 25 months) [see Adverse Reactions (6.1)]. Of the patients who experienced neuropathy and had data regarding resolution (n=373), 13% had complete resolution, and 87% of patients had residual neuropathy at last evaluation. Of the patients with residual neuropathy at last evaluation, 45% (146/326) had Grade ≥2 neuropathy.

Peripheral neuropathy occurred in 53% of the 720 patients treated with PADCEV as a single agent in clinical trials including 38% with sensory neuropathy, 8% with muscular weakness, and 7% with motor neuropathy. Thirty percent of patients experienced Grade 2 reactions and 5% experienced Grade 3-4 reactions. Peripheral neuropathy occurred in patients treated with PADCEV with or without preexisting peripheral neuropathy. The median time to onset of Grade ≥2 peripheral neuropathy was 4.9 months (range: 0.1 to 20 months). Neuropathy led to treatment discontinuation in 6% of patients [see Adverse Reactions (6.1)]. Of the patients who experienced neuropathy who had data regarding resolution (n=296), 11% had complete resolution, and 89% had residual neuropathy at the time of their last evaluation. Of the patients with residual neuropathy at last evaluation, 50% (132/262) had Grade ≥2 neuropathy.

Monitor patients for symptoms of new or worsening peripheral neuropathy and consider dose interruption or dose reduction of PADCEV when peripheral neuropathy occurs.

Permanently discontinue PADCEV in patients who develop Grade >3 peripheral neuropathy [see Dosage and Administration (2.2)].

5.5 Ocular Disorders

Ocular disorders were reported in 40% of the 384 patients treated with PADCEV as a single agent in clinical trials in which ophthalmologic exams were scheduled. The majority of these events involved the cornea and included events associated with dry eye such as keratitis, blurred vision, increased lacrimation, conjunctivitis, limbal stem cell deficiency, and keratopathy.

Dry eye symptoms occurred in 30% of patients, and blurred vision occurred in 10% of patients, during treatment with PADCEV. The median time to onset to symptomatic ocular disorder was 1.7 months (range: 0 to 30.6 months). Monitor patients for ocular disorders. Consider artificial tears for prophylaxis of dry eyes and ophthalmologic evaluation if ocular symptoms occur or do not resolve. Consider treatment with ophthalmic topical steroids, if indicated after an ophthalmic exam. Consider dose interruption or dose reduction of PADCEV for symptomatic ocular disorders.

5.6 Infusion Site Extravasation

Skin and soft tissue reactions secondary to extravasation have been observed after administration of PADCEV. Of the 720 patients treated with PADCEV as a single agent in clinical trials, 1% of patients experienced skin and soft tissue reactions, including 0.3% who experienced Grade 3-4 reactions. Reactions may be delayed. Erythema, swelling, increased temperature, and pain worsened until 2-7 days after extravasation and resolved within 1-4 weeks of peak. Two patients (0.3%) developed extravasation reactions with secondary cellulitis, bullae, or exfoliation. Ensure adequate venous access prior to starting PADCEV and monitor for possible extravasation during administration. If extravasation occurs, stop the infusion and monitor for adverse reactions.

5.7 Embryo-Fetal Toxicity

Based on the mechanism of action and findings in animals, PADCEV can cause fetal harm when administered to a pregnant woman. In animal reproduction studies, administration of enfortumab vedotin-ejfv to pregnant rats during the period of organogenesis caused maternal toxicity, embryo-fetal lethality, structural malformations and skeletal anomalies at maternal exposures similar to the clinical exposures at the recommended human dose of 1.25 mg/kg.

Advise patients of the potential risk to the fetus. Advise female patients of reproductive potential to use effective contraception during treatment with PADCEV and for 2 months after the last dose. Advise male patients with female partners of reproductive potential to use effective contraception during treatment with PADCEV and for 4 months after the last dose [see Use in Specific Populations (8.1, 8.3) and Clinical Pharmacology (12.1)].

6 ADVERSE REACTIONS

The following serious adverse reactions are described elsewhere in the labeling:

- Skin Reactions [see Boxed Warning, Warnings and Precautions (5.1)]
- Hyperglycemia [see Warnings and Precautions (5.2)]
- Pneumonitis/Interstitial Lung Disease (ILD) [see Warnings and Precautions (5.3)]
- Peripheral Neuropathy [see Warnings and Precautions (5.4)]
- Ocular Disorders [see Warnings and Precautions (5.5)]
- Infusion Site Extravasation [see Warnings and Precautions (5.6)]

6.1 Clinical Trials Experience

Because clinical trials are conducted under widely varying conditions, adverse reaction rates observed in the clinical trials of a drug cannot be directly compared to rates in the clinical trials of another drug and may not reflect the rates observed in practice.

The safety population described in the WARNINGS AND PRECAUTIONS reflect exposure to PADCEV 1.25 mg/kg in combination with intravenous pembrolizumab for the treatment of MIBC in 167 patients in EV-303 (NCT03924895) and for the treatment of locally advanced or mUC in 564 patients in EV-302 (NCT04223856) and EV-103 (NCT03288545); PADCEV as a single agent at 1.25 mg/kg in 720 patients in EV-301 (NCT03474107), EV-201 (NCT03219333), EV-203 (NCT04995419), EV-101 (NCT02091999), and EV-102 (NCT03070990). Ocular disorders reflect 384 patients in EV‑201, EV-101, and EV-102.

Among 167 patients receiving PADCEV in combination with intravenous pembrolizumab for the treatment of MIBC, the most common (≥20%) adverse reactions, including laboratory abnormalities, were increased glucose, decreased hemoglobin, increased aspartate aminotransferase, rash, increased alanine aminotransferase, fatigue, pruritus, increased creatinine, decreased sodium, decreased lymphocytes, peripheral neuropathy, increased potassium, alopecia, dysgeusia, diarrhea, decreased appetite, constipation, nausea, decreased phosphate, urinary tract infection, dry eye, and decreased weight.

Among 564 patients receiving PADCEV in combination with intravenous pembrolizumab for the treatment of locally advanced or mUC, 59% were exposed to PADCEV for ≥6 months, and 24% were exposed for ≥12 months. In this pooled population, the most common (≥20%) adverse reactions, including laboratory abnormalities, were increased aspartate aminotransferase, increased creatinine, rash, increased glucose, peripheral neuropathy, increased lipase, decreased lymphocytes, increased alanine aminotransferase, decreased hemoglobin, fatigue, decreased sodium, decreased phosphate, decreased albumin, pruritus, diarrhea, alopecia, decreased weight, decreased appetite, increased urate, decreased neutrophils, decreased potassium, dry eye, nausea, constipation, increased potassium, dysgeusia, urinary tract infection, and decreased platelets.

Among 720 patients receiving PADCEV as a single agent, 37% were exposed for ≥6 months, and 14% were exposed for ≥12 months. In this pooled population, the most common (≥20%) adverse reactions, including laboratory abnormalities, were increased glucose, increased aspartate aminotransferase, decreased lymphocytes, increased creatinine, rash, fatigue, peripheral neuropathy, decreased albumin, decreased hemoglobin, alopecia, decreased appetite, decreased neutrophils, decreased sodium, increased alanine aminotransferase, decreased phosphate, diarrhea, nausea, pruritus, increased urate, dry eye, dysgeusia, constipation, increased lipase, decreased weight, decreased platelets, abdominal pain, and dry skin.

The data described in the following section reflects exposure to PADCEV in combination with intravenous pembrolizumab from EV‑302, the dose escalation cohort, Cohort A and Cohort K of EV-103, and EV-303. Patients received PADCEV 1.25 mg/kg in combination with intravenous pembrolizumab until disease progression or unacceptable toxicity.

The data described in the following section also reflects exposure to PADCEV as a single agent from an open-label, randomized, trial (EV‑301) and Cohort 1 and Cohort 2 of an open-label, single arm, two cohort trial (EV-201). Patients received PADCEV 1.25 mg/kg until disease progression or unacceptable toxicity.

Neoadjuvant and Adjuvant Treatment of Cisplatin-Ineligible Patients with MIBC

EV-303

The safety of PADCEV in combination with intravenous pembrolizumab as neoadjuvant treatment and continued after radical cystectomy (RC) as adjuvant treatment was evaluated in an open-label, randomized, multicenter trial (EV-303) in patients with previously untreated MIBC who were ineligible for or declined cisplatin-based chemotherapy. Patients received PADCEV 1.25 mg/kg in combination with intravenous pembrolizumab (n=167) before and after RC with pelvic lymph node dissection (PLND) or RC with PLND alone (n=159) [see Clinical Studies (14)].

For the 167 patients who received PADCEV in the neoadjuvant phase, the median duration of exposure to PADCEV was 1.6 months (range: 0.03 to 2.8 months) and the median number of cycles of PADCEV was 3 (range: 1, 3) in the neoadjuvant phase. For the 92 patients who received PADCEV in the adjuvant phase, the median duration of exposure to PADCEV was 3.7 months (range: 0.03 to 7.6 months) and the median number of cycles of PADCEV was 6 (range: 1, 6) in the adjuvant phase. Across the combined neoadjuvant and adjuvant phases (n=167), the median number of cycles of PADCEV was 5 (range: 1, 9) out of a planned 9 cycles.

Table 5 summarizes the most common (≥20%) adverse reactions in EV-303.

Table 5. Adverse Reactions ≥20% (All Grades) in Patients Treated with PADCEV in Combination with Intravenous Pembrolizumab in EV-303
Adverse Reaction | PADCEV in combination with intravenous pembrolizumab before and after RC with PLND n=167 |  | RC with PLND alone n=159
Adverse Reaction | All Grades % | Grade 3-4 % | All Grades % | Grade 3-4 %
Skin and subcutaneous tissue disorders
Rash [Includes: multiple terms.] | 54 | 7 | 1.3 | 0
Pruritus | 47 | 3 | 0 | 0
Alopecia | 35 | 0.6 | 0 | 0
General disorders and administration site conditions
Fatigue | 47 | 4.2 | 6 | 0.6
Nervous system disorders
Peripheral neuropathy | 39 | 3 | 1.9 | 0
Dysgeusia | 35 | 0 | 0 | 0
Gastrointestinal disorders
Diarrhea | 34 | 5 | 3.1 | 1.3
Constipation | 28 | 1.8 | 8 | 0
Nausea | 26 | 1.2 | 8 | 0.6
Metabolism and nutrition disorders
Decreased appetite | 28 | 0.6 | 1.9 | 0
Infections and infestations
Urinary tract infection | 24 | 12 | 13 | 11
Eye disorders
Dry eye | 21 | 0 | 0 | 0
Investigations
Decreased weight | 20 | 0 | 3.1 | 0

Clinically relevant adverse reactions (<20%) include dry skin (15%), hypothyroidism (14%), vomiting (9%), pneumonitis/ILD (4.2%), skin hyperpigmentation (3%), infusion site extravasation (1.2%), and myasthenia gravis and myositis (0.6% each).

Table 6. Selected Laboratory Abnormalities Reported in ≥20% (All Grades) of Patients Treated with PADCEV in Combination with Intravenous Pembrolizumab in EV-303
Laboratory Abnormality | PADCEV in combination with intravenous pembrolizumab before and after RC with PLND |  | RC with PLND alone
Laboratory Abnormality | All Grades [The denominator used to calculate the rate of PADCEV in combination with intravenous pembrolizumab was 167 and the denominator used to calculate the rate for RC and PLND alone varied from 110 to 121 based on the number of patients with a baseline value and at least one post-treatment value.] % | Grade 3-4 % | All Grades % | Grade 3-4 %
Chemistry
Increased glucose | 72 | 12 | 24 | 1.7
Increased aspartate aminotransferase | 55 | 6 | 11 | 1.8
Increased alanine aminotransferase | 53 | 4.8 | 13 | 0.9
Increased creatinine | 47 | 8 | 31 | 2.5
Decreased sodium | 44 | 13 | 18 | 7
Increased potassium | 39 | 7 | 20 | 6
Decreased phosphate | 26 | 6 | 1.8 | 0
Hematology
Decreased hemoglobin | 60 | 13 | 48 | 8
Decreased lymphocytes | 40 | 8 | 17 | 1.7

Neoadjuvant Phase of EV-303

A total of 167 patients received at least one dose of PADCEV in combination with intravenous pembrolizumab as neoadjuvant treatment before receiving RC.

In the neoadjuvant phase, serious adverse reactions occurred in 27% of patients receiving PADCEV in combination with intravenous pembrolizumab. The most frequent (≥2%) serious adverse reactions were urinary tract infection (3.6%) and hematuria (2.4%). Fatal adverse reactions occurred in 1.2% of patients including myasthenia gravis and toxic epidermal necrolysis (0.6% each). Additional fatal adverse reactions were reported in 2.7% of patients in the post-surgery phase before adjuvant treatment started, including sepsis and intestinal obstruction (1.4% each).

Adverse reactions leading to discontinuation of PADCEV in the neoadjuvant phase occurred in 22% of patients. The most common adverse reactions (≥1%) leading to discontinuation of PADCEV were rash (4.8%), peripheral neuropathy (2.4%), and diarrhea, dysgeusia, fatigue, pruritus, and toxic epidermal necrolysis (1.2% each).

Adverse reactions leading to dose interruption of PADCEV in the neoadjuvant phase occurred in 29% of patients. The most common adverse reactions (≥2%) leading to dose interruption of PADCEV were rash (8%), neutropenia (3.6%), hyperglycemia (3%), and fatigue and peripheral neuropathy (2.4% each).

Adverse reactions leading to dose reduction of PADCEV in the neoadjuvant phase occurred in 13% of patients. The most common adverse reactions (≥1%) leading to dose reduction of PADCEV were rash (4.8%), pruritus (1.8%), and peripheral neuropathy, increase alanine aminotransferase, increased aspartate aminotransferase, decreased appetite, fatigue, neutropenia, and decreased weight (1.2% each).

Of the 167 patients in the PADCEV in combination with intravenous pembrolizumab arm who received neoadjuvant treatment, 7 (4.2%) patients did not receive surgery due to adverse reactions. The adverse reactions that led to cancellation of surgery were acute myocardial infarction, bile duct cancer, colon cancer, respiratory distress, urinary tract infection and the deaths due to myasthenia gravis and toxic epidermal necrolysis (0.6% each).

Of the 146 patients who received neoadjuvant treatment with PADCEV in combination with intravenous pembrolizumab and underwent RC, 6 (4.1%) patients experienced delay of surgery (defined as time from last neoadjuvant treatment to surgery exceeding 8 weeks) due to adverse reactions.

Adjuvant Phase of EV-303

Patients who did not proceed to surgery were ineligible for adjuvant treatment. Of the 149 patients who underwent surgery, 100 patients received adjuvant treatment with PADCEV in combination with intravenous pembrolizumab. Of the 49 patients who did not receive adjuvant treatment, discontinuation of treatment with PADCEV in combination with intravenous pembrolizumab prior to the adjuvant phase was due to an adverse event in 21 patients.

In the adjuvant phase, serious adverse reactions occurred in 43% of patients receiving PADCEV in combination with intravenous pembrolizumab. The most frequent (≥2%) serious adverse reactions were urinary tract infection (8%), acute kidney injury and pyelonephritis (5% each), urosepsis (4%), and hypokalemia, intestinal obstruction, and sepsis (2% each). Fatal adverse reactions occurred in 7% of patients, including urosepsis, hemorrhage intracranial, death, myocardial infarction, multiple organ dysfunction syndrome, and pneumonia pseudomonal (1% each).

Adverse reactions leading to discontinuation of PADCEV in the adjuvant phase occurred in 26% of patients. The most common adverse reactions (≥2%) leading to discontinuation of PADCEV were peripheral neuropathy (5%) and rash (4%).

Adverse reactions leading to dose interruption of PADCEV in the adjuvant phase occurred in 36% of patients. The most common adverse reactions (≥2%) leading to dose interruption of PADCEV were rash (6%), diarrhea and urinary tract infection (5% each), fatigue (4%), pruritus (3%), and peripheral neuropathy and pyelonephritis (2% each).

Adverse reactions leading to dose reduction of PADCEV in the adjuvant phase occurred in 7% of patients. The most common adverse reaction (≥2%) leading to dose reduction of PADCEV was weight decreased (2%).

Previously Untreated Locally Advanced or mUC

EV-302

The safety of PADCEV in combination with intravenous pembrolizumab was evaluated in an open-label, randomized, multicenter trial (EV-302) in patients with locally advanced or mUC. Patients received either PADCEV 1.25 mg/kg and pembrolizumab (n=440) or gemcitabine and platinum chemotherapy (either cisplatin or carboplatin) (n=433). Among patients who received PADCEV and pembrolizumab, the median duration of exposure for PADCEV was 7 months (range: 0.3 to 31.9 months).

Serious adverse reactions occurred in 50% of patients treated with PADCEV in combination with intravenous pembrolizumab. The most common serious adverse reactions (≥2%) were rash (6%), acute kidney injury (5%), pneumonitis/ILD (4.5%), urinary tract infection (3.6%), diarrhea (3.2%), pneumonia (2.3%), pyrexia (2%), and hyperglycemia (2%).

Fatal adverse reactions occurred in 3.9% of patients treated with PADCEV in combination with intravenous pembrolizumab including acute respiratory failure (0.7%), pneumonia (0.5%), and pneumonitis/ILD (0.2%).

Adverse reactions leading to discontinuation of PADCEV occurred in 35% of patients. The most common adverse reactions (≥2%) leading to discontinuation of PADCEV were peripheral neuropathy (15%), rash (4.1%), and pneumonitis/ILD (2.3%).

Adverse reactions leading to dose interruption of PADCEV occurred in 73% of patients. The most common adverse reactions (≥2%) leading to dose interruption of PADCEV were peripheral neuropathy (22%), rash (16%), COVID-19 (10%), diarrhea (5%), pneumonitis/ILD (4.8%), fatigue (3.9%), hyperglycemia (3.6%), increased alanine aminotransferase (3%), and pruritus (2.5%).

Adverse reactions leading to dose reduction of PADCEV occurred in 42% of patients. The most common adverse reactions (≥2%) leading to dose reduction of PADCEV were rash (16%), peripheral neuropathy (13%), and fatigue (2.7%).

Table 7 summarizes the most common (≥15%) adverse reactions in EV-302.

Table 7. Adverse Reactions ≥15% (All Grades) in Patients Treated with PADCEV in Combination with Intravenous Pembrolizumab in EV-302
Adverse Reaction | PADCEV in combination with intravenous pembrolizumab n=440 |  | Chemotherapy n=433
Adverse Reaction | All Grades % | Grade 3-4 % | All Grades % | Grade 3-4 %
Skin and subcutaneous tissue disorders
Rash [Includes: multiple terms.] | 68 | 15 | 15 | 0
Pruritus | 41 | 1.1 | 7 | 0
Alopecia | 35 | 0.5 | 8 | 0.2
Dry skin | 17 | 0.2 | 1 | 0
General disorders and administration site conditions
Fatigue | 51 | 6 | 57 | 7
Pyrexia | 18 | 0.7 | 16 | 1.2
Nervous system disorders
Peripheral neuropathy | 67 | 8 | 14 | 0
Dysgeusia | 21 | 0 | 9 | 0
Metabolism and nutrition disorders
Decreased appetite | 33 | 1.8 | 26 | 1.8
Gastrointestinal disorders
Diarrhea | 38 | 4.5 | 16 | 1.4
Nausea | 26 | 1.6 | 41 | 2.8
Constipation | 26 | 0 | 34 | 0.7
Investigations
Decreased weight | 33 | 3.6 | 9 | 0.2
Eye disorders
Dry eye | 24 | 0 | 2.1 | 0
Infections and infestations
Urinary tract infection | 21 | 5 | 19 | 8

Clinically relevant adverse reactions (<15%) include vomiting (12%), pneumonitis/ILD and hypothyroidism (10% each), blurred vision and skin hyperpigmentation (6% each), infusion site extravasation (1.8%), and myositis (0.5%).

Table 8. Selected Laboratory Abnormalities Reported in ≥15% (All Grades) of Patients Treated with PADCEV in Combination with Intravenous Pembrolizumab in EV-302
Laboratory Abnormality | PADCEV in combination with intravenous pembrolizumab |  | Chemotherapy
Laboratory Abnormality | All Grades [The denominator used to calculate the rate varied from 407 to 439 based on the number of patients with a baseline value and at least one post-treatment value.] % | Grade 3-4 % | All Grades % | Grade 3-4 %
Chemistry
Increased aspartate aminotransferase | 75 | 5 | 39 | 3
Increased creatinine | 71 | 3 | 68 | 3
Increased glucose | 66 | 14 | 54 | 5
Increased alanine aminotransferase | 59 | 5 | 49 | 3
Decreased sodium | 46 | 13 | 47 | 13
Decreased phosphate | 44 | 9 | 36 | 9
Decreased albumin | 39 | 2 | 35 | 0.5
Decreased potassium | 26 | 5 | 16 | 3
Increased potassium | 24 | 1 | 36 | 4
Increased calcium | 21 | 1 | 14 | 0.2
Hematology
Decreased lymphocytes | 58 | 15 | 59 | 17
Decreased hemoglobin | 53 | 7 | 89 | 33
Decreased neutrophils | 30 | 9 | 80 | 50

Previously Untreated Cisplatin-Ineligible Patients with Locally Advanced or mUC

EV-103

The safety of PADCEV was evaluated in combination with intravenous pembrolizumab in a multi cohort trial (EV-103) in 121 patients with locally advanced or mUC who were not eligible for cisplatin-containing chemotherapy and received at least one dose of PADCEV 1.25 mg/kg and pembrolizumab [see Clinical Studies (14)]. The median duration of exposure to PADCEV was 7 months (range: 0.6 to 33 months).

Serious adverse reactions occurred in 50% of patients treated with PADCEV in combination with intravenous pembrolizumab. The most common serious adverse reactions (≥2%) were acute kidney injury (7%), urinary tract infection (7%), urosepsis (5%), sepsis (3.3%), pneumonia (3.3%), hematuria (3.3%), pneumonitis/ILD (3.3%), urinary retention (2.5%), diarrhea (2.5%), myasthenia gravis (2.5%), myositis (2.5%), anemia (2.5%), and hypotension (2.5%).

Fatal adverse reactions occurred in 5% of patients treated with PADCEV in combination with intravenous pembrolizumab including sepsis (1.6%), bullous dermatitis (0.8%), myasthenia gravis (0.8%), and pneumonitis/ILD (0.8%).

Adverse reactions leading to discontinuation of PADCEV occurred in 36% of patients. The most common adverse reactions (≥2%) leading to discontinuation of PADCEV were peripheral neuropathy (20%) and rash (6%).

Adverse reactions leading to dose interruption of PADCEV occurred in 69% of patients. The most common adverse reactions (≥2%) leading to dose interruption of PADCEV were peripheral neuropathy (18%), rash (12%), increased lipase (6%), pneumonitis/ILD (6%), diarrhea (4.1%), acute kidney injury (3.3%), increased alanine aminotransferase (3.3%), fatigue (3.3%), neutropenia (3.3%), urinary tract infection (3.3%), increased amylase (2.5%), anemia (2.5%), COVID-19 (2.5%), hyperglycemia (2.5%), and hypotension (2.5%).

Adverse reactions leading to dose reduction of PADCEV occurred in 45% of patients. The most common adverse reactions (≥2%) leading to dose reduction of PADCEV were peripheral neuropathy (17%), rash (12%), fatigue (5%), neutropenia (5%), and diarrhea (4.1%).

Table 9 summarizes the most common (≥20%) adverse reactions in EV-103.

Table 9. Adverse Reactions ≥20% (All Grades) in Patients Treated with PADCEV in Combination with Intravenous Pembrolizumab in EV-103
Adverse Reaction | PADCEV in combination with intravenous pembrolizumab n=121
Adverse Reaction | All Grades % | Grade 3-4 %
Skin and subcutaneous tissue disorders
Rash [Includes: multiple terms.] | 71 | 21
Alopecia | 52 | 0
Pruritus | 40 | 3.3
Dry skin | 21 | 0.8
Nervous system disorders
Peripheral neuropathy | 65 | 3.3
Dysgeusia | 35 | 0
Dizziness | 23 | 0
General disorders and administration site conditions
Fatigue | 60 | 11
Peripheral edema | 26 | 0
Investigations
Decreased weight | 48 | 5
Gastrointestinal disorders
Diarrhea | 45 | 7
Nausea | 36 | 0.8
Constipation | 27 | 0
Metabolism and nutrition disorders
Decreased appetite | 38 | 0.8
Infections and infestations
Urinary tract infection | 30 | 12
Eye disorders
Dry eye | 25 | 0
Musculoskeletal and connective tissue disorders
Arthralgia | 23 | 1.7

Clinically relevant adverse reactions (<20%) include vomiting (20%), pyrexia (18%), hypothyroidism (11%), pneumonitis/ILD (10%), skin hyperpigmentation (8%), myasthenia gravis (2.5%), myositis (3.3%), and infusion site extravasation (0.8%).

Table 10. Selected Laboratory Abnormalities ≥20% (All Grades) in Patients Treated with PADCEV in Combination with Intravenous Pembrolizumab in EV-103
Laboratory Abnormality | PADCEV in combination with intravenous pembrolizumab
Laboratory Abnormality | All Grades [The denominator used to calculate the rate varied from 114 to 121 based on the number of patients with a baseline value and at least one post-treatment value.] % | Grade 3-4 %
Chemistry
Increased glucose | 74 | 13
Increased aspartate aminotransferase | 73 | 9
Increased creatinine | 69 | 3.3
Decreased sodium | 60 | 19
Increased alanine aminotransferase | 60 | 7
Increased lipase | 59 | 32
Decreased albumin | 59 | 4.2
Decreased phosphate | 51 | 15
Decreased potassium | 35 | 8
Increased potassium | 27 | 1.7
Increased calcium | 27 | 4.2
Hematology
Decreased hemoglobin | 69 | 15
Decreased lymphocytes | 64 | 17
Decreased neutrophils | 32 | 12

Previously Treated Locally Advanced or mUC

EV-301

The safety of PADCEV was evaluated as a single agent in EV-301 in patients with locally advanced or mUC (n=296) who received at least one dose of PADCEV 1.25 mg/kg and who were previously treated with a PD-1 or PD-L1 inhibitor and a platinum-based chemotherapy [see Clinical Studies (14)]. Routine ophthalmologic exams were not conducted in EV-301. The median duration of exposure to PADCEV was 5 months (range: 0.5 to 19 months).

Serious adverse reactions occurred in 47% of patients treated with PADCEV. The most common serious adverse reactions (≥2%) were urinary tract infection, acute kidney injury (7% each), and pneumonia (5%). Fatal adverse reactions occurred in 3% of patients, including multiorgan dysfunction (1%), hepatic dysfunction, septic shock, hyperglycemia, pneumonitis/ILD, and pelvic abscess (0.3% each).

Adverse reactions leading to discontinuation occurred in 17% of patients; the most common adverse reactions (≥2%) leading to discontinuation were peripheral neuropathy (5%) and rash (4%).

Adverse reactions leading to dose interruption occurred in 61% of patients; the most common adverse reactions (≥4%) leading to dose interruption were peripheral neuropathy (23%), rash (11%), and fatigue (9%).

Adverse reactions leading to dose reduction occurred in 34% of patients; the most common adverse reactions (≥2%) leading to dose reduction were peripheral neuropathy (10%), rash (8%), decreased appetite (3%), and fatigue (3%).

Table 11 summarizes the most common (≥15%) adverse reactions in EV-301.

Table 11. Adverse Reactions (≥15%) in Patients Treated with PADCEV in EV-301
Adverse Reaction | PADCEV n=296 |  | Chemotherapy n=291
Adverse Reaction | All Grades % | Grade 3-4 % | All Grades % | Grade 3-4 %
Skin and subcutaneous tissue disorders
Rash [Includes: multiple terms.] | 54 | 14 | 20 | 0.3
Alopecia | 47 | 0 | 38 | 0
Pruritus | 34 | 2 | 7 | 0
Dry skin | 17 | 0 | 4 | 0
General disorders and administration site conditions
Fatigue | 50 | 9 | 40 | 7
Pyrexia | 22 | 2 | 14 | 0
Nervous system disorders
Peripheral neuropathy | 50 | 5 | 34 | 3
Dysgeusia | 26 | 0 | 8 | 0
Metabolism and nutrition disorders
Decreased appetite | 41 | 5 | 27 | 2
Gastrointestinal disorders
Diarrhea | 35 | 4 | 23 | 2
Nausea | 30 | 1 | 25 | 2
Constipation | 28 | 1 | 25 | 2
Abdominal Pain | 20 | 1 | 14 | 3
Musculoskeletal and connective tissue disorders
Musculoskeletal Pain | 25 | 2 | 35 | 5
Eye Disorders
Dry eye | 24 | 0.7 | 6 | 0.3
Infections and infestations
Urinary Tract Infection | 17 | 6 | 13 | 3
Vascular disorders
Hemorrhage | 17 | 3 | 13 | 2
Investigations
Decreased weight | 16 | 0.3 | 7 | 0

Clinically relevant adverse reactions (<15%) include vomiting (14%), increased aspartate aminotransferase (12%), hyperglycemia (10%), increased alanine aminotransferase (9%), skin hyperpigmentation (8%), pneumonitis/ILD (3%), and infusion site extravasation (0.7%).

Table 12. Selected Laboratory Abnormalities Reported in ≥15% (Grades 2-4) or ≥5% (Grade 3-4) of Patients Treated with PADCEV in EV-301
Laboratory Abnormality | PADCEV [The denominator used to calculate the rate varied from 262 to 287 based on the number of patients with a baseline value and at least one post-treatment value.] |  | Chemotherapy
Laboratory Abnormality | Grades 2-4 % | Grade 3-4 % | Grades 2-4 % | Grade 3-4 %
Hematology
Decreased lymphocytes | 41 | 14 | 34 | 18
Decreased hemoglobin | 28 | 4 | 42 | 14
Decreased neutrophils | 27 | 12 | 25 | 17
Chemistry
Decreased phosphate | 39 | 8 | 24 | 6
Increased glucose (non-fasting) | 33 | 9 | 27 | 6
Increased creatinine | 18 | 2 | 13 | 0
Decreased potassium | 16 | 2 | 7 | 3
Increased lipase | 13 | 8 | 7 | 4
Decreased sodium | 8 | 8 | 5 | 5

EV-201, Cohort 1

The safety of PADCEV was evaluated as a single agent in EV-201, Cohort 1 in patients (n=125) with locally advanced or mUC who had received prior treatment with a PD-1 or PD-L1 inhibitor and platinum-based chemotherapy [see Clinical Studies (14)]. Patients received PADCEV 1.25 mg/kg on Days 1, 8, and 15 of a 28-day cycle until disease progression or unacceptable toxicity. The median duration of exposure to PADCEV was 4.6 months (range: 0.5 to 15.6 months).

Serious adverse reactions occurred in 46% of patients treated with PADCEV. The most common serious adverse reactions (≥3%) were urinary tract infection (6%), cellulitis (5%), febrile neutropenia (4%), diarrhea (4%), sepsis (3%), acute kidney injury (3%), dyspnea (3%), and rash (3%). Fatal adverse reactions occurred in 3.2% of patients, including acute respiratory failure, aspiration pneumonia, cardiac disorder, sepsis, and pneumonitis/ILD (each 0.8%).

Adverse reactions leading to discontinuation occurred in 16% of patients; the most common adverse reaction leading to discontinuation was peripheral neuropathy (6%).

Adverse reactions leading to dose interruption occurred in 64% of patients; the most common adverse reactions leading to dose interruption were peripheral neuropathy (18%), rash (9%), and fatigue (6%).

Adverse reactions leading to dose reduction occurred in 34% of patients; the most common adverse reactions leading to dose reduction were peripheral neuropathy (12%), rash (6%), and fatigue (4%).

Table 13 summarizes the All Grades and Grades 3-4 adverse reactions reported in patients in EV-201, Cohort 1.

Table 13. Adverse Reactions Reported in ≥15% (All Grades) or ≥5% (Grade 3-4) of Patients Treated with PADCEV in EV-201 Cohort 1
Adverse Reaction | PADCEV n=125
Adverse Reaction | All Grades % | Grade 3-4 %
General disorders and administration site conditions
Fatigue [Includes: multiple terms.] | 56 | 6
Nervous system disorders
Peripheral neuropathy | 56 | 4
Dysgeusia | 42 | 0
Metabolism and nutrition disorders
Decreased appetite | 52 | 2
Skin and subcutaneous tissue disorders
Rash | 52 | 13
Alopecia | 50 | 0
Dry skin | 26 | 0
Pruritus | 26 | 2
Gastrointestinal disorders
Nausea | 45 | 3
Diarrhea | 42 | 6
Vomiting | 18 | 2
Eye disorders
Dry eye | 40 | 0

Clinically relevant adverse reactions (<15%) include skin hyperpigmentation (14%), herpes zoster (3%), pneumonitis/ILD (2%), and infusion site extravasation (2%).

Table 14. Selected Laboratory Abnormalities Reported in ≥15% (Grades 2-4) or ≥5% (Grade 3-4) of Patients Treated with PADCEV in EV-201, Cohort 1
Laboratory Abnormality | PADCEV
Laboratory Abnormality | Grades 2-4 [Denominator for each laboratory parameter is based on the number of patients with a baseline and post-treatment laboratory value available for 121 or 122 patients.] % | Grade 3-4 %
Hematology
Decreased hemoglobin | 34 | 10
Decreased lymphocytes | 32 | 10
Decreased neutrophils | 14 | 5
Chemistry
Decreased phosphate | 34 | 10
Increased glucose (non-fasting) | 27 | 8
Increased creatinine | 20 | 2
Decreased potassium | 19 [Includes Grade 1 (potassium 3.0-3.5 mmol/L) – Grade 4.] | 1
Increased lipase | 14 | 9
Decreased sodium | 8 | 8
Increased urate | 7 | 7

EV-201, Cohort 2

The safety of PADCEV was evaluated as a single agent in EV-201, Cohort 2 in patients with locally advanced or mUC (n=89) who received at least one dose of PADCEV 1.25 mg/kg and had prior treatment with a PD-1 or PD-L1 inhibitor and were not eligible for cisplatin-based chemotherapy. The median duration of exposure was 5.98 months (range: 0.3 to 24.6 months).

Serious adverse reactions occurred in 39% of patients treated with PADCEV. The most common serious adverse reactions (≥3%) were pneumonia, sepsis, and diarrhea (5% each). Fatal adverse reactions occurred in 8% of patients, including acute kidney injury (2.2%), metabolic acidosis, sepsis, multiorgan dysfunction, pneumonia, and pneumonitis/ILD (1.1% each).

Adverse reactions leading to discontinuation occurred in 20% of patients; the most common adverse reaction (≥2%) leading to discontinuation was peripheral neuropathy (7%).

Adverse reactions leading to dose interruption occurred in 60% of patients; the most common adverse reactions (≥3%) leading to dose interruption were peripheral neuropathy (19%), rash (9%), fatigue (8%), diarrhea (5%), increased aspartate aminotransferase (3%), and hyperglycemia (3%).

Adverse reactions leading to dose reduction occurred in 49% of patients; the most common adverse reactions (≥3%) leading to dose reduction were peripheral neuropathy (19%), rash (11%), and fatigue (7%).

Table 15 summarizes the All Grades and Grades 3-4 adverse reactions reported in patients in EV-201, Cohort 2.

Table 15. Adverse Reactions ≥15% (All Grades) or ≥5% (Grades 3-4) in Patients Treated with PADCEV in EV‑201, Cohort 2
Adverse Reaction | PADCEV n=89
Adverse Reaction | All Grades (%) | Grades 3-4 (%)
Skin and subcutaneous tissue disorders
Rash [Includes: multiple terms.] | 66 | 17
Alopecia | 53 | 0
Pruritus | 35 | 3
Dry skin | 19 | 1
Nervous system disorders
Peripheral neuropathy | 58 | 8
Dysgeusia | 29 | 0
General disorders and administration site conditions
Fatigue | 48 | 11
Metabolism and nutrition disorders
Decreased appetite | 40 | 6
Hyperglycemia | 16 | 9
Gastrointestinal disorders
Diarrhea | 36 | 8
Nausea | 30 | 1
Investigations
Decreased weight | 35 | 1
Eye disorders
Dry eye | 30 | 0

Clinically relevant adverse reactions (<15%) include vomiting (13%), increased aspartate aminotransferase (12%), increased lipase (11%), increased alanine aminotransferase (10%), skin hyperpigmentation (4%), pneumonitis/ILD (4%), and infusion site extravasation (1%).

Table 16. Selected Laboratory Abnormalities Reported in ≥15% (Grades 2-4) or ≥5% (Grades 3-4) of Patients Treated with PADCEV in EV-201, Cohort 2
Laboratory Abnormality | PADCEV n=88 [Based on the number of patients with a baseline value and at least one post-treatment value.]
Laboratory Abnormality | Grades 2-4 % | Grade 3-4 %
Hematology
Decreased lymphocytes | 43 | 15
Decreased hemoglobin | 34 | 5
Decreased neutrophils | 20 | 9
Chemistry
Increased glucose (non-fasting) | 36 | 13
Decreased phosphate | 25 | 7
Increased creatinine | 23 | 3
Increased lipase | 18 | 11
Increased urate | 9 | 9
Increased potassium | 8 | 6
Decreased sodium | 7 | 7

6.2 Post Marketing Experience

The following adverse reactions have been identified during post-approval use of PADCEV. Because these reactions are reported voluntarily from a population of uncertain size, it is not always possible to reliably estimate their frequency or establish a causal relationship to drug exposure.

Skin and subcutaneous tissue disorders: Epidermal necrosis, Stevens-Johnson syndrome, and toxic epidermal necrolysis [see Warnings and Precautions (5.1)].

7 DRUG INTERACTIONS

7.1 Effects of Other Drugs on PADCEV

Dual P-gp and Strong CYP3A4 Inhibitors

Concomitant use with dual P-gp and strong CYP3A4 inhibitors may increase unconjugated MMAE exposure [see Clinical Pharmacology (12.3)], which may increase the incidence or severity of PADCEV toxicities. Closely monitor patients for signs of toxicity when PADCEV is given concomitantly with dual P-gp and strong CYP3A4 inhibitors.

8 USE IN SPECIFIC POPULATIONS

8.1 Pregnancy

Risk Summary

Based on the mechanism of action and findings in animals, PADCEV can cause fetal harm when administered to a pregnant woman [see Clinical Pharmacology (12.1)]. There are no available human data on PADCEV use in pregnant women to inform a drug-associated risk. In an animal reproduction study, administration of enfortumab vedotin-ejfv to pregnant rats during organogenesis caused maternal toxicity, embryo-fetal lethality, structural malformations, and skeletal anomalies at maternal exposures similar to the exposures at the recommended human dose of 1.25 mg/kg (see Data). Advise patients of the potential risk to the fetus.

The background risk of major birth defects and miscarriage for the indicated population is unknown. In the U.S. general population, the estimated background risk of major birth defects and miscarriage in clinically recognized pregnancies is 2%-4% and 15%-20%, respectively.

Data

Animal Data

In a rat pilot embryo-fetal development study, administration of enfortumab vedotin-ejfv on gestation day 6 and 13 during the period of organogenesis resulted in a complete litter loss in all pregnant rats at the maternally toxic dose of 5 mg/kg (approximately 3 times the exposure at the recommended human dose). A dose of 2 mg/kg (similar to the exposure at the recommended human dose) resulted in maternal toxicity, embryo-fetal lethality, and structural malformations that included gastroschisis, malrotated hindlimb, absent forepaw, malpositioned internal organs, and fused cervical arch. Additionally, skeletal anomalies (asymmetric, fused, incompletely ossified, and misshapen sternebrae, misshapen cervical arch, and unilateral ossification of the thoracic centra) and decreased fetal weight were observed.

8.2 Lactation

Risk Summary

There are no data on the presence of enfortumab vedotin-ejfv in human milk, the effects on the breastfed child, or the effects on milk production. Because of the potential for serious adverse reactions in a breastfed child, advise lactating women not to breastfeed during treatment with PADCEV and for 3 weeks after the last dose.

8.3 Females and Males of Reproductive Potential

Pregnancy Testing

Verify pregnancy status in females of reproductive potential prior to initiating PADCEV treatment [see Use in Specific Populations (8.1)].

Contraception

Females

PADCEV can cause fetal harm when administered to a pregnant woman [see Use in Specific Populations (8.1)]. Advise females of reproductive potential to use effective contraception during treatment with PADCEV and for 2 months after the last dose.

Males

Advise male patients with female partners of reproductive potential to use effective contraception during treatment with PADCEV and for 4 months after the last dose.

Infertility

Females

Based on findings in animal studies with MMAE-containing antibody-drug conjugates (ADCs), PADCEV may impair female fertility. The effect on fertility is reversible [see Nonclinical Toxicology (13.1)].

Males

Based on findings from animal studies, PADCEV may impair male fertility [see Nonclinical Toxicology (13.1)].

8.4 Pediatric Use

Safety and effectiveness of PADCEV in pediatric patients have not been established.

8.5 Geriatric Use

Of the 167 patients treated with PADCEV in combination with intravenous pembrolizumab for the treatment of MIBC, 37% (n=61) were 65-74 years and 46% (n=77) were 75 years or older. Of the 564 patients treated with PADCEV in combination with intravenous pembrolizumab for the treatment of locally advanced or mUC, 44% (n=247) were 65‑74 years and 26% (n=144) were 75 years or older. Of the 720 patients treated with PADCEV as a single agent in clinical trials, 39% (n=282) were 65‑74 years and 24% (n=170) were 75 years or older. No overall differences in effectiveness were observed between patients 65 years of age or older and younger patients.

Patients 75 years of age or older treated with PADCEV in combination with intravenous pembrolizumab for the treatment of MIBC experienced a higher incidence of fatal adverse reactions than younger patients. The incidence of fatal adverse reactions was 4% in patients younger than 75 and 12% in patients 75 years or older.

Patients 75 years of age or older treated with PADCEV in combination with intravenous pembrolizumab for the treatment of locally advanced or mUC experienced a higher incidence of fatal adverse reactions than younger patients. The incidence of fatal adverse reactions was 4% in patients younger than 75 and 7% in patients 75 years or older.

Patients 75 years of age or older treated with PADCEV as a single agent experienced a higher incidence of fatal adverse reactions than younger patients. The incidence of fatal adverse reactions was 6% in patients younger than 75 years, and 11% in patients 75 years or older.

No significant difference was observed in the pharmacokinetics of PADCEV between patients 65 years and older and younger patients [see Clinical Pharmacology (12.3)].

8.6 Hepatic Impairment

Avoid the use of PADCEV in patients with moderate or severe hepatic impairment (total bilirubin >1.5 × ULN and any AST). PADCEV has only been studied in a limited number of patients with moderate or severe hepatic impairment [see Clinical Pharmacology (12.3)]. In another ADC that contains MMAE, the frequency of ≥ Grade 3 adverse reactions and deaths was greater in patients with moderate (Child-Pugh B) or severe (Child-Pugh C) hepatic impairment compared to patients with normal hepatic function.

11 DESCRIPTION

Enfortumab vedotin-ejfv is a Nectin-4 directed antibody-drug conjugate (ADC) comprised of a fully human anti-Nectin-4 IgG1 kappa monoclonal antibody (AGS-22C3) conjugated to the small molecule microtubule disrupting agent, monomethyl auristatin E (MMAE) via a protease-cleavable maleimidocaproyl valine-citrulline (vc) linker (SGD-1006). Conjugation takes place on cysteine residues that comprise the interchain disulfide bonds of the antibody to yield a product with a drug-to-antibody ratio of approximately 3.8:1. The molecular weight is approximately 152 kDa.

Figure 1. Structural Formula

Approximately 4 molecules of MMAE are attached to each antibody molecule. Enfortumab vedotin-ejfv is produced by chemical conjugation of the antibody and small molecule components. The antibody is produced by mammalian (Chinese hamster ovary) cells and the small molecule components are produced by chemical synthesis.

PADCEV (enfortumab vedotin-ejfv) for injection is provided as a sterile, preservative-free, white to off-white lyophilized powder in single-dose vials for intravenous use. PADCEV is supplied as a 20 mg per vial and a 30 mg per vial and requires reconstitution with Sterile Water for Injection, USP, (2.3 mL and 3.3 mL, respectively) resulting in a clear to slightly opalescent, colorless to slightly yellow solution with a final concentration of 10 mg/mL [see Dosage and Administration (2.3)]. After reconstitution, each vial allows the withdrawal of 2 mL (20 mg) and 3 mL (30 mg). Each mL of reconstituted solution contains 10 mg of enfortumab vedotin-ejfv, histidine (1.4 mg), histidine hydrochloride monohydrate (2.31 mg), polysorbate 20 (0.2 mg), and trehalose dihydrate (55 mg) with a pH of 6.0.

12 CLINICAL PHARMACOLOGY

12.1 Mechanism of Action

Enfortumab vedotin-ejfv is an ADC. The antibody is a human IgG1 kappa directed against Nectin-4, an adhesion protein located on the surface of cells. The small molecule, MMAE, is a microtubule-disrupting agent, attached to the antibody via a protease-cleavable linker. Nonclinical data suggest that the anticancer activity of enfortumab vedotin-ejfv is due to the binding of the ADC to Nectin-4-expressing cells, followed by internalization of the ADC-Nectin-4 complex, and the release of MMAE via proteolytic cleavage. Release of MMAE disrupts the microtubule network within the cell, subsequently inducing cell cycle arrest and apoptosis. The combination of enfortumab vedotin-ejfv with a PD-1 blocking antibody resulted in up-regulation of immune function and increased anti-tumor activity in syngeneic mouse tumor models expressing Nectin-4.

12.2 Pharmacodynamics

In an exposure-response analysis for safety, higher enfortumab vedotin-ejfv exposure was associated with higher incidence of some adverse reactions (e.g., Grade ≥2 peripheral neuropathy, Grade ≥3 hyperglycemia). The exposure‑response relationship for efficacy has not been fully characterized.

Cardiac Electrophysiology

At the recommended dose, PADCEV had no large QTc prolongation (>20 msec).

12.3 Pharmacokinetics

Enfortumab vedotin-ejfv (ADC) pharmacokinetics were characterized after single and multiple doses in patients with solid tumors.

The pharmacokinetics of the ADC and unconjugated MMAE were consistent when assessed following PADCEV administration as a single agent and in combination with intravenous pembrolizumab after 1 treatment cycle.

The exposure parameters of the ADC and unconjugated MMAE (the cytotoxic component of enfortumab vedotin-ejfv) are summarized in Table 17 below. Peak ADC concentrations were observed near the end of intravenous infusion while peak unconjugated MMAE concentrations were observed approximately 2 days after PADCEV dosing. Minimal accumulation of the ADC and unconjugated MMAE was observed following repeat administration of PADCEV in patients. Steady-state concentrations of the ADC were reached after 1 treatment cycle for the ADC as a single agent and in combination with intravenous pembrolizumab.

Table 17. Exposure Parameters of the ADC and Unconjugated MMAE after First Treatment Cycle of 1.25 mg/kg of PADCEV Dose of Days 1, 8, and 15
Parameter | ADC; Mean (± SD) | Unconjugated MMAE; Mean (± SD)
Cmax | 28 (6.1) µg/mL | 5.5 (3.0) ng/mL
AUC0-28d | 110 (26) µg∙d/mL | 85 (50) ng∙d/mL
Ctrough,0-28d | 0.31 (0.18) µg/mL | 0.81 (0.88) ng/mL
Cmax = maximum concentration, AUC0-28d = area under the concentration-time curve from time zero to 28 days, Ctrough,0-28d = pre-dose concentration on day 28.

Distribution

The estimated mean steady-state volume of distribution of the ADC was 12.8 L following administration of PADCEV. In vitro, plasma protein binding of unconjugated MMAE ranged from 68% to 82%.

Elimination

The ADC and unconjugated MMAE exhibited multi-exponential declines with an elimination half-life of 3.6 days and 2.6 days, respectively. The mean clearance (CL) of the ADC and unconjugated MMAE was 0.11 L/h and 2.11 L/h, respectively. Elimination of unconjugated MMAE appeared to be limited by its rate of release from the ADC.

Metabolism

Catabolism of the ADC has not been studied in humans; however, it is expected to undergo catabolism to small peptides, amino acids, unconjugated MMAE, and unconjugated MMAE-related catabolites. The ADC releases MMAE via proteolytic cleavage, and unconjugated MMAE is primarily metabolized by CYP3A4 in vitro.

Excretion

The excretion of the ADC is not fully characterized. Following a single-dose of another ADC that contains unconjugated MMAE, 17% of the total unconjugated MMAE administered was recovered in feces and 6% in urine over a 1-week period, primarily as unchanged form. A similar excretion profile of unconjugated MMAE is expected after PADCEV administration.

Specific Populations

No clinically significant differences in the pharmacokinetics of the ADC or unconjugated MMAE were identified based on age (24 to 90 years), sex, race (White, Asian, or Black), renal impairment, and mild hepatic impairment (total bilirubin of 1 to 1.5 × ULN and any AST, or total bilirubin ≤ULN and AST >ULN). The effect of end-stage renal disease with or without dialysis and moderate or severe hepatic impairment (total bilirubin >1.5 × ULN and any AST) on the pharmacokinetics of the ADC or unconjugated MMAE is unknown.

Drug Interaction Trials

No clinical trials evaluating the drug-drug interaction potential of the ADC have been conducted.

Physiologically Based Pharmacokinetic (PBPK) Modeling Predictions:

Dual P-gp and Strong CYP3A4 Inhibitor: Concomitant use of PADCEV with ketoconazole (a dual P-gp and strong CYP3A4 inhibitor) is predicted to increase unconjugated MMAE Cmax by 15% and AUC by 38%.

Dual P-gp and Strong CYP3A4 Inducer: Concomitant use of PADCEV with rifampin (a dual P-gp and strong CYP3A4 inducer) is predicted to decrease unconjugated MMAE Cmax by 28% and AUC by 53%.

Sensitive CYP3A Substrates: Concomitant use of PADCEV is predicted not to affect exposure to midazolam (a sensitive CYP3A substrate).

In Vitro Studies

Transporter Systems: MMAE is a substrate of P-glycoprotein (P-gp) and is not an inhibitor of P-gp.

12.6 Immunogenicity

The observed incidence of anti-drug antibody (ADA) is highly dependent on the sensitivity and specificity of the assay. Differences in assay methods preclude meaningful comparisons of the incidence of ADA in the studies described below with the incidence of ADA in other studies, including those of PADCEV or of other enfortumab vedotin products.

ADA was evaluated during the treatment periods (up to 5.5 years) in nine clinical studies of PADCEV as a single agent or in combination with intravenous pembrolizumab at the approved recommended dosages. Anti‑enfortumab vedotin-ejfv antibodies developed in:

- 3.7% (25/684) of patients who received PADCEV as a single agent.
- 1.3% (2/156) of patients who received PADCEV in combination with intravenous pembrolizumab for the treatment of MIBC.
- 7% (34/485) of patients who received PADCEV in combination with intravenous pembrolizumab for the treatment of locally advanced or mUC.

Because of the low occurrence of ADA, the effect of the ADA on the pharmacokinetics, pharmacodynamics, safety, and/or effectiveness of PADCEV is unknown.

13 NONCLINICAL TOXICOLOGY

13.1 Carcinogenesis, Mutagenesis, Impairment of Fertility

Carcinogenicity studies with enfortumab vedotin-ejfv or the small molecule cytotoxic agent (MMAE) have not been conducted.

MMAE was genotoxic in the rat bone marrow micronucleus study through an aneugenic mechanism. This effect is consistent with the pharmacological effect of MMAE as a microtubule-disrupting agent. MMAE was not mutagenic in the bacterial reverse mutation assay (Ames test) or the L5178Y mouse lymphoma forward mutation assay.

Fertility studies with enfortumab vedotin-ejfv or MMAE have not been conducted. However, results of repeat-dose toxicity studies indicate the potential for enfortumab vedotin-ejfv to impair female and male reproductive function and fertility.

In repeat-dose toxicology studies conducted in rats for up to 13 weeks, doses ≥2 mg/kg enfortumab vedotin-ejfv (at exposures similar to the exposures at the recommended human dose) resulted in decreases in testes and epididymis weights, seminiferous tubule degeneration, spermatid/spermatocyte depletion in the testes and cell debris, sperm granuloma, and hypospermia/abnormal spermatids in the epididymis. Findings in the testes and epididymis did not reverse by the end of the recovery period.

MMAE-containing ADCs have been associated with adverse ovarian effects when administered to sexually immature animals. Adverse effects included decrease in, or absence of, secondary and tertiary ovarian follicles after weekly administration to cynomolgus monkeys in studies of 4-week duration. These effects showed a trend towards recovery 6 weeks after the end of dosing; no changes were observed in primordial follicles.

14 CLINICAL STUDIES

14.1 Urothelial Cancer

Neoadjuvant and Adjuvant Treatment of Cisplatin-Ineligible Patients with MIBC

EV-303

The efficacy of PADCEV in combination with intravenous pembrolizumab as neoadjuvant treatment and then continued after RC as adjuvant treatment was evaluated in EV-303 (NCT03924895), an open-label, randomized, multicenter trial that enrolled patients with previously untreated MIBC with predominant urothelial carcinoma histology and who were candidates for radical cystectomy (RC) with pelvic lymph node dissection (PLND) but were ineligible for or refused cisplatin-based chemotherapy. The study excluded patients with primary non-bladder (i.e., ureter, urethral, or renal pelvis) cancer of the urothelium and those with active autoimmune disease that required systemic therapy within 2 years of treatment or a medical condition that required immunosuppression.

Randomization was stratified by tumor stage (T2N0 vs T3/T4aN0 vs T1-T4aN1), cisplatin-eligibility (cisplatin-ineligible vs cisplatin-eligible but declined), and geographic region (United States vs European Union vs Rest of World).

Patients were randomized 1:1 to receive:

- Neoadjuvant PADCEV 1.25 mg/kg as an intravenous infusion on Days 1 and 8 in combination with intravenous pembrolizumab 200 mg as an intravenous infusion on Day 1 of a 21-day cycle for 3 cycles prior to surgery, followed by adjuvant PADCEV for up to 6 cycles and intravenous pembrolizumab for up to 14 cycles (21 days per cycle) (n=170).
- Immediate RC and PLND alone (n=174).

Treatment continued until completion of the treatment, disease progression, not undergoing or refusal of RC and PLND, disease recurrence in the adjuvant phase, or unacceptable toxicity. Assessment of tumor status, including CT/MRI, was performed at baseline, within 5 weeks prior to RC and PLND, and at 6 weeks post-surgery. Following RC and PLND, assessment of tumor status, including cystoscopy and urine cytology for patients who did not undergo surgery, was performed every 12 weeks up to 2 years, and every 24 weeks thereafter.

The median age was 73 years (range: 46 to 87 years); 78% were male; 78% were White, 16% were Asian, 3.2% were multiple, 1.2% were Black or African American, 0.3% American Indian or Alaska Native, and race in 1.2% was missing; 91% were not Hispanic or Latino, 6% were Hispanic or Latino, and 2.9% were not reported. Patients had a baseline Eastern Cooperative Oncology Group (ECOG) performance status of 0 (57%), 1 (29%), or 2 (14%). Eighteen percent were T2N0, 77% T3/T4aN0, and 4.9% T1-T4aN1. Among the 281 patients who were ineligible for cisplatin, 72% had baseline creatinine clearance of 30-59 mL/min, 17% had ECOG PS of 2, 21% had Grade 2 or greater hearing loss, 3.9% had NYHA Class III heart failure, and 13% met more than one cisplatin-ineligibility criterion. Ninety-one percent of patients had pure urothelial carcinoma histology; 4.4% had urothelial carcinoma with squamous differentiation, 2.6% had urothelial carcinoma with glandular differentiation, and 2% had urothelial carcinoma with other variant histology.

In the overall population, 149 (88%) patients in the PADCEV in combination with intravenous pembrolizumab arm and 156 (90%) patients in the RC and PLND alone arm underwent RC and PLND.

The trial was not designed to isolate the effect of PADCEV in combination with intravenous pembrolizumab in each phase (neoadjuvant or adjuvant) of treatment.

The major efficacy outcome measure was event-free survival (EFS) as assessed by blinded independent central review (BICR). Overall survival (OS) and pathological complete response (pCR) rate as assessed by blinded independent pathology review were additional efficacy outcome measures.

The trial demonstrated statistically significant improvements in EFS and OS in patients treated with neoadjuvant and adjuvant PADCEV in combination with intravenous pembrolizumab compared with RC and PLND alone.

Table 18 and Figures 2-3 summarize the efficacy results for EV-303.

Table 18. Efficacy Results in EV-303
Endpoint | PADCEV with intravenous pembrolizumab before and after RC with PLND n=170 | RC with PLND alone n=174
Event-Free Survival [EFS is defined as time from randomization to the first of: disease progression preventing curative surgery, failure to undergo surgery for participants with muscle invasive residual disease, incomplete surgical resection, local or distant recurrence after surgery, or death.]
Number (%) of patients with events | 48 (28) | 95 (55)
Median in months [Based on Kaplan-Meier estimates.] (95% CI) | NR (37.3, NR) | 15.7 (10.3, 20.5)
Hazard ratio [Based on stratified Cox regression model.] (95% CI) | 0.40 (0.28, 0.57)
p-value [Based on stratified log-rank test.] | <0.0001
Overall Survival
Number (%) of patients with events | 38 (22) | 68 (39)
Median in months (95% CI) | NR (NR, NR) | 41.7 (31.8, NR)
Hazard ratio (95% CI) | 0.50 (0.33, 0.74)
p-value | 0.0002
NR = Not Reached.

Figure 2. Kaplan-Meier Plot of Event-Free Survival, EV-303

Figure 3. Kaplan-Meier Plot of Overall Survival, EV-303

The trial demonstrated a statistically significant difference in pCR rate (57.1% [95% CI: 49.3, 64.6] vs. 8.6% [95% CI: 4.9, 13.8]; p<0.0001).

Previously Untreated Locally Advanced or mUC

EV-302

The efficacy of PADCEV in combination with intravenous pembrolizumab was evaluated in EV-302 (NCT04223856), an open label, randomized, multicenter trial that enrolled 886 patients with locally advanced or mUC who received no prior systemic therapy for locally advanced or metastatic disease. Patients with active CNS metastases, ongoing sensory or motor neuropathy Grade ≥2, or uncontrolled diabetes defined as hemoglobin A1C (HbA1c) ≥8% or HbA1c ≥7% with associated diabetes symptoms were excluded.

Patients were randomized 1:1 to receive either:

- PADCEV 1.25 mg/kg on Days 1 and 8 of a 21-day cycle followed by intravenous pembrolizumab 200 mg on Day 1 of a 21‑day cycle. Treatment was continued until disease progression or unacceptable toxicity. In the absence of disease progression or unacceptable toxicity, pembrolizumab was continued for up to 2 years.
- Gemcitabine 1000 mg/m^2 on Days 1 and 8 of a 21-day cycle with cisplatin 70 mg/m^2 or carboplatin (AUC = 4.5 or 5) on Day 1 of a 21-day cycle. Treatment was continued until disease progression or unacceptable toxicity for up to 6 cycles.

Randomization was stratified by cisplatin eligibility, PD-L1 expression, and presence of liver metastases.

The median age was 69 years (range: 22 to 91 years); 77% were male; 67% were White, 22% were Asian, 1% were Black or African American, and 10% were unknown or other; 12% were Hispanic or Latino. Patients had a baseline Eastern Cooperative Oncology Group (ECOG) performance status of 0 (49%), 1 (47%), or 2 (3%). Forty-seven percent of patients had a documented baseline HbA1c of <5.7%. At baseline, 95% of patients had metastatic urothelial cancer, including 72% with visceral and 22% with liver metastases, and 5% had locally advanced urothelial cancer. Eighty-five percent of patients had urothelial carcinoma (UC) histology including 6% with UC mixed squamous differentiation and 2% with UC mixed other histologic variants. Forty-six percent of patients were considered cisplatin-ineligible and 54% were considered cisplatin-eligible at time of randomization.

The major efficacy outcome measures were overall survival (OS) and progression-free survival (PFS) as assessed by blinded independent central review (BICR) according to Response Evaluation Criteria in Solid Tumors (RECIST) v1.1. Additional efficacy outcome measures included objective response rate (ORR) as assessed by BICR.

The trial demonstrated statistically significant improvements in OS, PFS, and ORR for patients randomized to PADCEV in combination with intravenous pembrolizumab as compared to platinum-based chemotherapy. Efficacy results were consistent across all stratified patient subgroups. Table 19 and Figures 4-5 summarize the efficacy results for EV-302.

Table 19. Efficacy Results in EV-302
Endpoint | PADCEV with intravenous pembrolizumab n=442 | Cisplatin or carboplatin with gemcitabine n=444
Overall Survival
Number (%) of patients with events | 133 (30.1) | 226 (50.9)
Median in months (95% CI) | 31.5 (25.4, NE) | 16.1 (13.9, 18.3)
Hazard ratio (95% CI) [Based on a stratified Cox proportional hazards model.] | 0.47 (0.38, 0.58)
p-value [Based on stratified log-rank test.] , [Two-sided p-value.] | <0.0001
Progression-Free Survival
Number (%) of patients with events | 223 (50.5) | 307 (69.1)
Median in months (95% CI) | 12.5 (10.4, 16.6) | 6.3 (6.2, 6.5)
Hazard ratio (95% CI) | 0.45 (0.38, 0.54)
p-value, | <0.0001
Confirmed Objective Response Rate [Includes only patients with measurable disease at baseline (n=437 for PADCEV in combination with intravenous pembrolizumab, n=441 for chemotherapy).]
ORR (%) (95% CI) | 67.7 (63.1, 72.1) | 44.4 (39.7, 49.2)
p-value, [Cochran-Mantel-Haenszel test (CMH) controlling for stratification factors.] | <0.0001
Complete response rate (%) | 29.1 | 12.5
Partial response rate (%) | 38.7 | 32.0
NE = Not estimable.

Figure 4. Kaplan-Meier Plot of Overall Survival, EV-302

Figure 5. Kaplan-Meier Plot of Progression-Free Survival, EV-302

Cisplatin-Ineligible Patients with Previously Untreated Locally Advanced or mUC

EV-103

The efficacy of PADCEV in combination with intravenous pembrolizumab was evaluated in EV-103 (NCT03288545), an open-label, multi-cohort (dose escalation cohort, Cohort A, Cohort K) trial in patients with locally advanced or metastatic urothelial cancer who were ineligible for cisplatin-containing chemotherapy and received no prior systemic therapy for locally advanced or metastatic disease. Patients with active CNS metastases, ongoing sensory or motor neuropathy Grade ≥2, or uncontrolled diabetes defined as hemoglobin A1C (HbA1c) ≥8% or HbA1c ≥7% with associated diabetes symptoms were excluded from participating in the trial.

Patients in the dose escalation cohort (n=5), Cohort A (n=40), and Cohort K (n=76) received PADCEV 1.25 mg/kg as an IV infusion on Days 1 and 8 of a 21-day cycle followed by intravenous pembrolizumab 200 mg on Day 1 of a 21-day cycle. Patients were treated until disease progression or unacceptable toxicity.

A total of 121 patients received PADCEV in combination with intravenous pembrolizumab. The median age was 71 years (range: 51 to 91 years); 74% were male; 85% were White, 5% were Black, 4% were Asian, and 6% were other, unknown, or not reported. Ten percent of patients were Hispanic or Latino. Forty-five percent of patients had an ECOG performance status of 1 and 15% had an ECOG performance status of 2. Forty-seven percent of patients had a documented baseline HbA1c of <5.7%. Reasons for cisplatin ineligibility included: 60% with baseline creatinine clearance of 30-59 mL/min, 10% with ECOG PS of 2, 13% with Grade 2 or greater hearing loss, and 16% with more than one cisplatin-ineligibility criteria.

At baseline, 97.5% of patients had metastatic urothelial cancer and 2.5% of patients had locally advanced urothelial cancer. Thirty-seven percent of patients had upper tract disease. Eighty-four percent of patients had visceral metastasis at baseline including 22% with liver metastases. Thirty-nine percent of patients had transitional cell carcinoma (TCC) histology; 13% had TCC with squamous differentiation and 48% had TCC with other histologic variants.

The major efficacy outcome measures were ORR and DoR as assessed by BICR according to RECIST v1.1.

The median follow-up time for the dose escalation cohort + Cohort A was 44.7 months (range: 0.7 to 52.4 months) and for Cohort K was 14.8 months (range: 0.6 to 26.2 months).

Efficacy results are presented in Table 20 below.

Table 20. Efficacy Results in EV-103, Combined Dose Escalation Cohort, Cohort A, and Cohort K
Endpoint | PADCEV in combination with intravenous pembrolizumab n=121
Confirmed ORR (95% CI) | 68% (58.7, 76.0)
Complete response rate | 12%
Partial response rate | 55%

The median duration of response for the dose escalation cohort + Cohort A was 22.1 months (range: 1.0+ to 46.3+ months) and for Cohort K was not reached (range: 1.2 to 24.1+ months).

Previously Treated Locally Advanced or mUC

EV-301

The efficacy of PADCEV as a single agent was evaluated in EV-301 (NCT03474107), an open-label, randomized, multicenter trial that enrolled 608 patients with locally advanced or mUC who received prior treatment with a PD-1 or PD-L1 inhibitor and platinum-based chemotherapy. Patients were randomized 1:1 to receive either PADCEV 1.25 mg/kg on Days 1, 8, and 15 of a 28-day cycle or investigator’s choice of chemotherapy. Randomization was stratified by ECOG PS (0 vs 1), region of world (Western Europe vs US vs Rest of World), and presence of liver metastasis.

Patients were excluded if they had active central nervous system (CNS) metastases, ongoing sensory or motor neuropathy ≥ Grade 2, or uncontrolled diabetes defined as hemoglobin A1C (HbA1c) ≥8% or HbA1c ≥7% with associated diabetes symptoms.

The median age was 68 years (range: 30 to 88 years) and 77% were male. Racial demographics were reported as White (52%), Asian (33%), Black (0.7%), Native Hawaiian or Other Pacific Islander (0.2%), or not reported (15%). Nine percent of patients were Hispanic or Latino. All patients had a baseline ECOG performance status of 0 (40%) or 1 (60%). Thirty‑four percent of patients had tumors located in the upper tract that included the renal pelvis and ureter. Eighty percent of patients had visceral metastases including 31% with liver metastases. Seventy-six percent of patients had pure TCC histology; 14% had TCC with other histologic variants; and 10% had other tumor histologies including adenocarcinoma and squamous cell carcinoma. The median number of prior therapies was 2 (range 1 to ≥3). Sixty-three percent of patients received prior cisplatin-based regimens, 26% received prior carboplatin-based regimens, and an additional 11% received both cisplatin and carboplatin-based regimens. Patients on the control arm received docetaxel (38%), paclitaxel (36%), or vinflunine (25%).

The major efficacy outcome measures were OS, PFS, and ORR assessed by investigator using RECIST v1.1. Efficacy results were consistent across all stratified patient subgroups.

Table 21 and Figures 6-7 summarize the efficacy results for EV-301.

Table 21. Efficacy Results in EV-301
Endpoint | PADCEV n=301 | Chemotherapy n=307
Overall Survival [Based on log-rank test. Stratification factors were ECOG PS, region and liver metastasis.]
Number (%) of patients with events | 134 (44.5) | 167 (54.4)
Median in months (95% CI) | 12.9 (10.6, 15.2) | 9.0 (8.1, 10.7)
Hazard ratio (95% CI) | 0.70 (0.56, 0.89)
p-value | 0.0014
Progression-Free Survival
Number (%) of patients with events | 201 (66.8) | 231 (75.2)
Median in months (95% CI) | 5.6 (5.3, 5.8) | 3.7 (3.5, 3.9)
Hazard ratio (95% CI) | 0.62 (0.51, 0.75)
p-value | <0.0001
Overall Response Rate (CR + PR) [Based on Cochran-Mantel-Haenszel test. Stratification factors were ECOG PS, region and liver metastasis.]
ORR (%) (95% CI) | 40.6 (34.9, 46.5) | 17.9 (13.7, 22.8)
p-value | <0.0001
Complete response rate (%) | 4.9 | 2.7
Partial response rate (%) | 35.8 | 15.2

Figure 6. Kaplan-Meier Plot of Overall Survival, EV-301

Figure 7. Kaplan-Meier Plot of Progression-Free Survival, EV-301

EV-201, Cohort 1

The efficacy of PADCEV as a single agent was also investigated in Cohort 1 of EV-201 (NCT03219333), a single-arm, multi-cohort, multicenter trial that enrolled 125 patients with locally advanced or mUC who received prior treatment with a PD-1 or PD-L1 inhibitor and a platinum-based chemotherapy. Patients were excluded if they had active central nervous system (CNS) metastases, ongoing sensory or motor neuropathy ≥ Grade 2, heart failure, or uncontrolled diabetes defined as hemoglobin A1C (HbA1c) ≥8% or HbA1c ≥7% with associated diabetes symptoms.

PADCEV was administered at a dose of 1.25 mg/kg, as an intravenous (IV) infusion on Days 1, 8, and 15 of each 28-day cycle.

The median age was 69 years (range: 40 to 84 years) and 70% were male. Racial demographics were reported as White (85%), Asian (9%), Black (2%), Other (0.8%), or not reported (4%). Four percent of patients were Hispanic or Latino. All patients had a baseline Eastern Cooperative Oncology Group (ECOG) performance status of 0 (32%) or 1 (68%). Ninety percent of patients had visceral metastases including 40% with liver metastases. Approximately two-thirds (67%) of patients had pure transitional cell carcinoma (TCC) histology; 33% had TCC with other histologic variants. The median number of prior systemic therapies was 3 (range: 1 to 6). Sixty-six percent of patients received prior cisplatin-based regimens, 26% received prior carboplatin-based regimens, and an additional 8% received both cisplatin and carboplatin‑based regimens.

The major efficacy outcome measures were confirmed objective response rate (ORR) and duration of response (DOR) assessed by BICR using RECIST v1.1.

Efficacy results are presented in Table 22.

Table 22. Efficacy Results in EV-201, Cohort 1 (BICR Assessment)
Endpoint | PADCEV n=125
Confirmed ORR (95% CI) | 44% (35.1, 53.2)
Complete Response Rate (CR) | 12%
Partial Response Rate (PR) | 32%
Median [Based on patients (n=55) with a response by BICR.] Duration of Response, months (95% CI) | 7.6 (6.3, NE)
NE = not estimable.

Previously Treated Cisplatin-Ineligible Patients with Locally Advanced or mUC

EV-201, Cohort 2

The efficacy of PADCEV as a single agent was also evaluated in Cohort 2 of EV-201, a single-arm, multi-cohort, multicenter trial in 89 patients with locally advanced or mUC who received prior treatment with a PD-1 or PD-L1 inhibitor and were cisplatin-ineligible and did not receive platinum in the locally advanced or metastatic setting. Patients were excluded if they had active CNS metastases, ongoing sensory or motor neuropathy ≥ Grade 2, heart failure, or uncontrolled diabetes defined as hemoglobin A1C (HbA1c) ≥8% or HbA1c ≥7% with associated diabetes symptoms.

PADCEV was administered at a dose of 1.25 mg/kg, as an intravenous (IV) infusion on Days 1, 8, and 15 of each 28-day cycle.

The median age was 75 years (range: 49 to 90 years), 74% were male. Racial demographics were reported as White (70%), Asian (22%), or not reported (8%). One percent of patients were Hispanic or Latino. Patients had a baseline ECOG performance status of 0 (42%), 1 (46%), and 2 (12%). Forty-three percent of patients had tumors located in the upper tract that included the renal pelvis and ureter. Seventy-nine percent of patients had visceral metastases and 24% had liver metastases.

Reasons for cisplatin ineligibility included: 66% with baseline creatinine clearance of 30-59 mL/min, 7% with ECOG PS of 2, 15% with Grade 2 or greater hearing loss, and 12% with more than one cisplatin-ineligibility criteria. Seventy percent of patients had TCC histology; 13% had TCC with squamous differentiation and 17% had TCC with other histologic variants.

The median number of prior systemic therapies was 1 (range: 1 to 4).

Efficacy results are presented in Table 23 below.

Table 23. Efficacy Results in EV-201, Cohort 2 (BICR Assessment)
Endpoint | PADCEV; n=89
Confirmed ORR (95% CI) | 51% (39.8, 61.3)
Complete Response Rate (CR) | 22%
Partial Response Rate (PR) | 28%
Median [Based on patients (n=45) with a response by BICR.] Duration of Response, months (95% CI) | 13.8 (6.4, NE)
NE = not estimable.

15 REFERENCES

1. "OSHA Hazardous Drugs." OSHA. http://www.osha.gov/SLTC/hazardousdrugs/index.html

16 HOW SUPPLIED/STORAGE AND HANDLING

How Supplied

PADCEV (enfortumab vedotin-ejfv) 20 mg and 30 mg are supplied as a sterile, preservative-free, white to off-white lyophilized powder in single-dose vials. PADCEV vials are available in the following packages:

- Carton of one 20 mg single-dose vial (NDC 51144-020-01)
- Carton of one 30 mg single-dose vial (NDC 51144-030-01)

Storage

Store PADCEV vials refrigerated at 2ºC to 8ºC (36ºF to 46ºF) in the original carton. Do not freeze. Do not shake.

Special Handling

PADCEV is a hazardous drug. Follow applicable special handling and disposal procedures.^1

17 PATIENT COUNSELING INFORMATION

Advise the patient to read the FDA-approved patient labeling (Patient Information).

Skin Reactions

Inform patients that severe skin reactions including SJS and TEN with fatal outcomes have occurred after administration of PADCEV, predominantly during the first cycle of treatment but may occur later.

Advise patients to contact their healthcare provider immediately if they develop new target lesions, progressively worsening skin reactions, severe blistering, or peeling of the skin [see Boxed Warning and Warnings and Precautions (5.1)].

Hyperglycemia

Inform patients about the risk of hyperglycemia and how to recognize associated symptoms [see Warnings and Precautions (5.2)].

Pneumonitis/ILD

Advise patients to immediately report new or worsening respiratory symptoms [see Warnings and Precautions (5.3)].

Peripheral Neuropathy

Inform patients to report to their healthcare provider any numbness and tingling of the hands or feet or muscle weakness [see Warnings and Precautions (5.4)].

Ocular disorders

Advise patients to contact their healthcare provider if they experience any visual changes [see Warnings and Precautions (5.5)]. In order to prevent or treat dry eyes, advise patients to use artificial tear substitutes.

Infusion Site Extravasation

Inform patients that infusion site reactions have occurred after administration of PADCEV. These reactions generally occurred immediately after administration but, in some instances, had a delayed onset (e.g., 24 hours). Instruct patients to contact their healthcare provider immediately if they experience an infusion site reaction [see Warnings and Precautions (5.6)].

Embryo-Fetal Toxicity

Advise pregnant women and females of reproductive potential of the potential risk to the fetus. Advise females to inform their healthcare providers of a known or suspected pregnancy [see Warnings and Precautions (5.7) and Use in Specific Populations (8.1)].

Females and Males of Reproductive Potential

Advise female patients of reproductive potential to use effective contraception during treatment with PADCEV and for 2 months after the last dose. Advise male patients with female partners of reproductive potential to use effective contraception during treatment with PADCEV and for 4 months after the last dose [see Use in Specific Populations (8.3)].

Lactation

Advise women not to breastfeed during treatment with PADCEV and for 3 weeks after the last dose [see Use in Specific Populations (8.2)].

Infertility

Advise females and males of reproductive potential that PADCEV may impair fertility [see Use in Specific Populations (8.3)].

Manufactured and Marketed by:
Astellas Pharma US, Inc.
Northbrook, Illinois 60062

Distributed and Marketed by:
Seagen Inc.
Bothell, WA 98021
1-855-4SEAGEN

U.S. License 2124
PADCEV is a registered trademark jointly owned by Agensys, Inc. and Seagen Inc.
©2025 Agensys, Inc. and Seagen Inc.
08368-EV-US

PATIENT INFORMATION

PADCEV® (PAD-sev)

(enfortumab vedotin-ejfv)

for injection

If your healthcare provider prescribes PADCEV in combination with the medicines pembrolizumab or pembrolizumab and berahyaluronidase alfa-pmph, also read the Medication Guide that comes with these medicines for additional important information.

What is the most important information I should know about PADCEV?

PADCEV may cause serious side effects, including:

Skin reactions. Skin reactions including severe skin reactions have happened in people treated with PADCEV and may be more common when PADCEV is given with pembrolizumab. In some cases, these severe skin reactions have caused death. Most severe skin reactions occurred during the first cycle of treatment but may happen later. Your healthcare provider will monitor you, may stop your treatment with PADCEV completely or for a period of time (temporarily), may change your dose, and may prescribe medicines if you get skin reactions. Tell your healthcare provider right away if you develop any of these signs of a new or worsening skin reaction:

- target lesions (skin reactions that look like rings)
- rash or itching that continues to get worse
- blistering or peeling of the skin

- painful sores or ulcers in mouth or nose, throat, or genital area
- fever or flu-like symptoms
- swollen lymph nodes

See “What are the possible side effects of PADCEV?” for more information about side effects.

What is PADCEV?

PADCEV is a prescription medicine used to treat adults with bladder cancer and cancers of the urinary tract (renal pelvis, ureter, or urethra).

- PADCEV may be used with pembrolizumab or pembrolizumab and berahyaluronidase alfa-pmph before and after the surgical removal of your bladder when:
  - your bladder cancer has spread into the muscle layer of the bladder (muscle invasive bladder cancer [MIBC]) but not to other parts of the body, and
  - you are not able to receive chemotherapy that contains the medicine cisplatin.
- PADCEV may be used with pembrolizumab or pembrolizumab and berahyaluronidase alfa-pmph when your bladder or urinary tract cancer has spread or cannot be removed by surgery (locally advanced or metastatic).
- PADCEV may be used alone when your bladder or urinary tract cancer has spread or cannot be removed by surgery (locally advanced or metastatic) if you:
  - have received PD-1 or PD-L1 immunotherapy medicine and chemotherapy that contains platinum, or
  - are not able to receive a chemotherapy that contains cisplatin and you have received 1 or more prior therapies.

It is not known if PADCEV is safe and effective in children.

Before receiving PADCEV, tell your healthcare provider about all of your medical conditions, including if you:

- are currently experiencing numbness or tingling in your hands or feet
- have a history of high blood sugar or diabetes
- have liver problems
- are pregnant or plan to become pregnant. PADCEV can harm your unborn baby. Tell your healthcare provider right away if you become pregnant or think you may be pregnant during treatment with PADCEV.
Females who are able to become pregnant:
  - Your healthcare provider should do a pregnancy test before you start treatment with PADCEV.
  - You should use an effective method of birth control during your treatment and for at least 2 months after the last dose of PADCEV.
Males with a female sexual partner who is able to become pregnant:
  - If your female partner is pregnant, PADCEV can harm the unborn baby.
  - You should use an effective method of birth control during your treatment and for at least 4 months after the last dose of PADCEV.
- are breastfeeding or plan to breastfeed. It is not known if PADCEV passes into your breast milk. Do not breastfeed during treatment and for 3 weeks after the last dose of PADCEV.

Tell your healthcare provider about all the medicines you take, including prescription and over-the-counter medicines, vitamins, and herbal supplements. Taking PADCEV with certain other medicines may cause side effects.

How will I receive PADCEV?

- PADCEV will be given to you by intravenous (IV) infusion into your vein over 30 minutes.
- PADCEV is given over periods of time called “cycles”.
- If you receive PADCEV with pembrolizumab or pembrolizumab and berahyaluronidase alfa-pmph:
  - Each cycle is 21 days.
  - You will receive PADCEV on days 1 and 8 of every cycle.
- If you receive PADCEV alone:
  - Each PADCEV cycle is 28 days.
  - You will receive PADCEV on days 1, 8, and 15 of every cycle.
- Your healthcare provider will decide how many treatment cycles you need.
- Your healthcare provider may do blood tests regularly during treatment with PADCEV.

What are the possible side effects of PADCEV?

PADCEV may cause serious side effects, including:

- See “What is the most important information I should know about PADCEV?”
- High blood sugar (hyperglycemia). An increase in blood sugar is common during treatment with PADCEV. Severe high blood sugar, a serious condition called diabetic ketoacidosis (DKA), and death have happened in people with and without diabetes, treated with PADCEV. Tell your healthcare provider right away if you get any symptoms of high blood sugar, including:

- frequent urination
- increased thirst
- blurred vision
- confusion
- it becomes harder to control your blood sugar

- drowsiness
- loss of appetite
- fruity smell on your breath
- nausea, vomiting, or stomach pain

- Lung problems. PADCEV may cause severe or life-threatening inflammation of the lungs that can lead to death. These severe problems may happen more often when PADCEV is given in combination with pembrolizumab. Tell your healthcare provider right away if you get new or worsening symptoms, including trouble breathing, shortness of breath, or cough.
- Nerve problems. Nerve problems called peripheral neuropathy are common during treatment with PADCEV and can also sometimes be severe. Nerve problems may happen more often when PADCEV is given in combination with pembrolizumab. Tell your healthcare provider right away if you get new or worsening numbness or tingling in your hands or feet or muscle weakness.
- Eye problems. Certain eye problems are common during treatment with PADCEV. Tell your healthcare provider right away if you get dry eyes, increased tearing, blurred vision, or any vision changes. You may use artificial tear substitutes to help prevent or treat dry eyes.
- Leakage of PADCEV out of your vein into the tissues around your infusion site (extravasation). If PADCEV leaks from the injection site or the vein into the nearby skin and tissues, it could cause an infusion site reaction. These reactions can happen right after you receive an infusion, but sometimes may happen days after your infusion. Tell your healthcare provider or get medical help right away if you notice any redness, swelling, itching, blister, peeling skin, or discomfort at the infusion site.

Your healthcare provider may decrease your dose of PADCEV, or temporarily or completely stop your treatment with PADCEV if you get severe side effects.

The most common side effects of PADCEV when used in combination with pembrolizumab include:

- changes in liver function and kidney function tests
- rash. See “What is the most important information I should know about PADCEV?”
- increased sugar (glucose) in the blood. See “High blood sugar (hyperglycemia)” above.
- numbness or tingling in your hands or feet. See “Nerve problems” above.

- increased lipase (a test done to check your pancreas)
- decreased white blood cell, red blood cell, and platelet counts
- tiredness
- decreased sodium, phosphate, and protein (albumin) in the blood
- itching
- diarrhea
- hair loss

- decreased weight
- decreased appetite
- increased uric acid in the blood
- increased or decreased potassium
- dry eye. See “Eye problems” above.
- nausea
- constipation
- change in sense of taste
- urinary tract infection

The most common side effects of PADCEV when used alone include:

- increased sugar (glucose) in the blood. See “High blood sugar (hyperglycemia)” above.
- changes in liver and kidney function tests
- decreased white blood cell, red blood cell, and platelet counts
- rash. See “What is the most important information I should know about PADCEV?”
- tiredness

- numbness or tingling in your hands or feet. See “Nerve problems” above.
- decreased protein (albumin), sodium, and phosphate in the blood
- hair loss
- decreased appetite
- diarrhea
- nausea
- itching

- increased uric acid in the blood
- dry eye. See “Eye problems” above.
- change in sense of taste
- constipation
- increased lipase (a blood test done to check your pancreas)
- decreased weight
- stomach (abdominal) pain
- dry skin

PADCEV may cause fertility problems in females and males, which may affect the ability to have children. Talk to your healthcare provider if you have concerns about fertility.

These are not all of the possible side effects of PADCEV.

Call your doctor for medical advice about side effects. You may report side effects to FDA at 1-800-FDA-1088.

General information about the safe and effective use of PADCEV.

Medicines are sometimes prescribed for purposes other than those listed in a Patient Information leaflet. You can ask your pharmacist or healthcare provider for information about PADCEV that is written for healthcare professionals.

What are the ingredients in PADCEV?

Active ingredient: enfortumab vedotin-ejfv

Inactive ingredients: histidine, histidine hydrochloride monohydrate, polysorbate 20, and trehalose dihydrate.

Manufactured and Marketed by: Astellas Pharma US, Inc., Northbrook, Illinois 60062

Distributed and Marketed by: Seagen Inc., Bothell, WA 98021

U.S. License 2124

PADCEV is a registered trademark jointly owned by Agensys, Inc. and Seagen Inc.

©2025 Agensys, Inc. and Seagen Inc.

For more information, go to www.padcev.com or call 1-888-472-3238

08368-EV-US

This Patient Information has been approved by the U.S. Food and Drug Administration. Revised: 11/2025

PACKAGE/LABEL PRINCIPAL DISPLAY PANEL

NDC 51144-020-01

PADCEV®

enfortumab vedotin-ejfv

FOR INJECTION

20 mg/vial

CAUTION: Cytotoxic Agent

For intravenous infusion use only

Must reconstitute and dilute before use

Single-dose vial. Discard unused portion

Rx Only

PACKAGE/LABEL PRINCIPAL DISPLAY PANEL

NDC 51144-030-01

PADCEV®

enfortumab vedotin-ejfv

FOR INJECTION

30 mg/vial

CAUTION: Cytotoxic Agent

For intravenous infusion use only

Must reconstitute and dilute before use

Single-dose vial. Discard unused portion

Rx Only